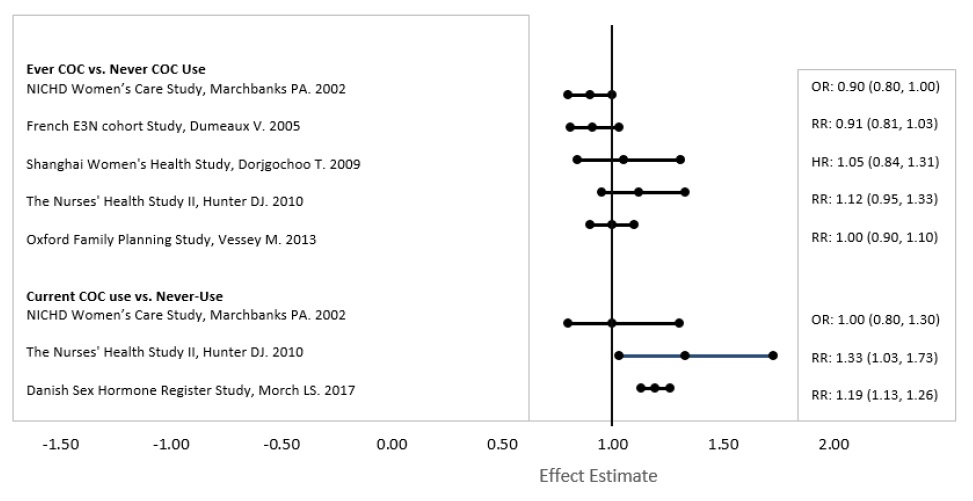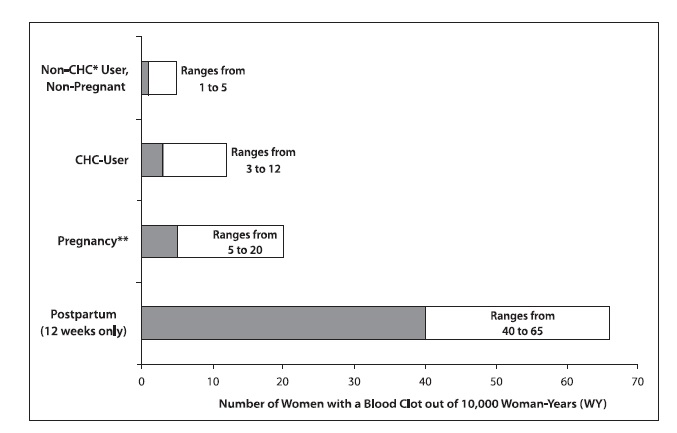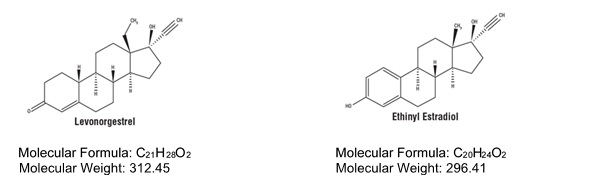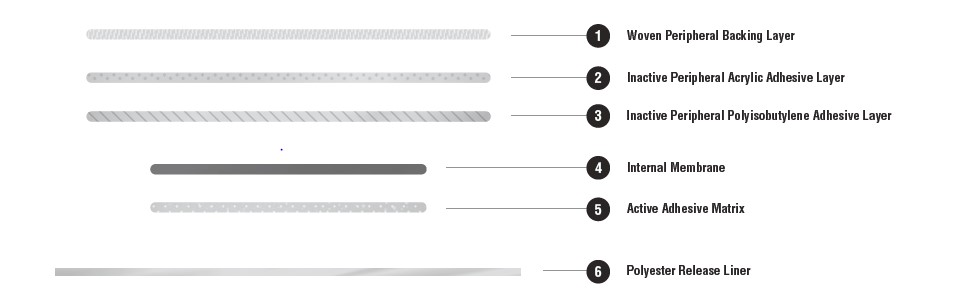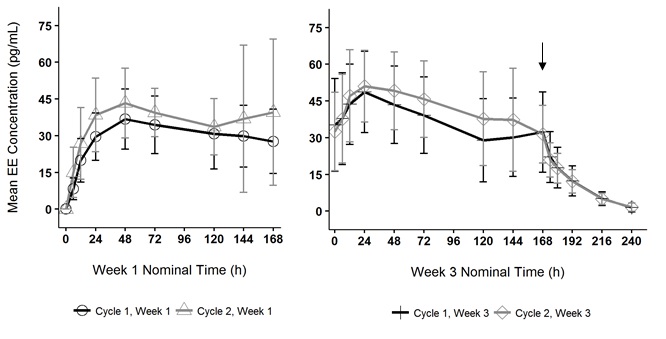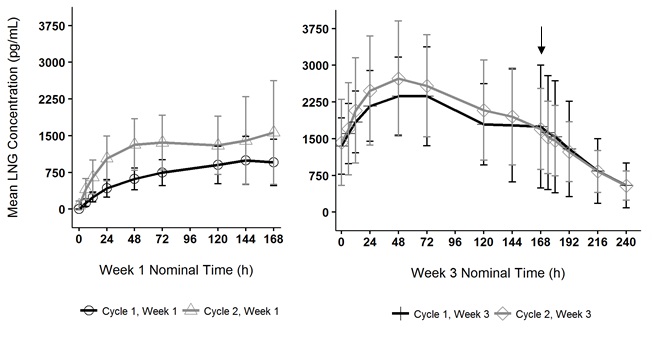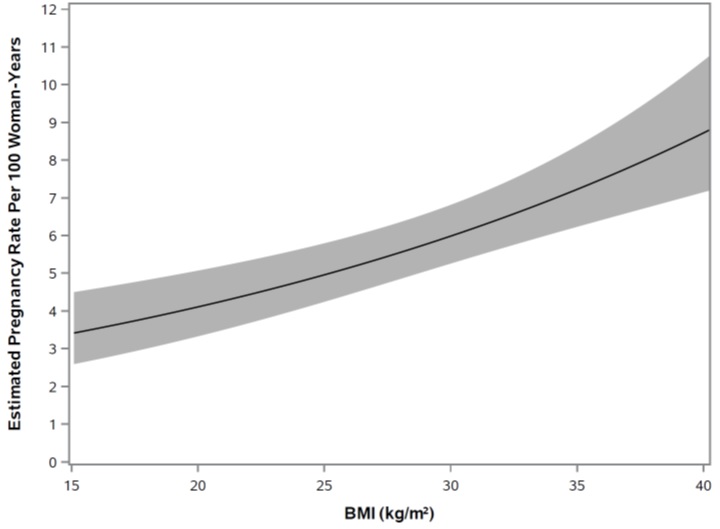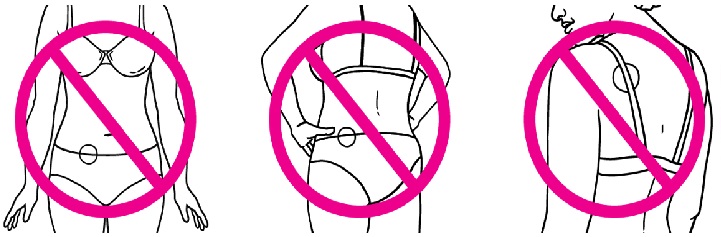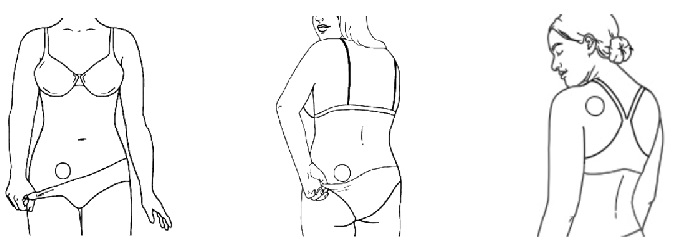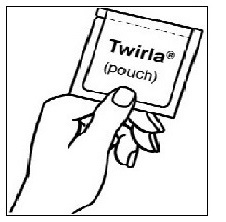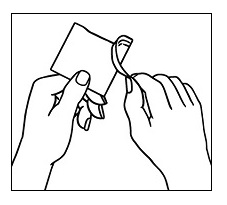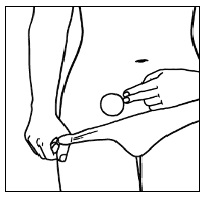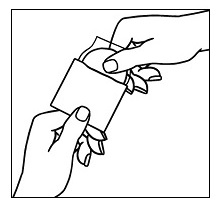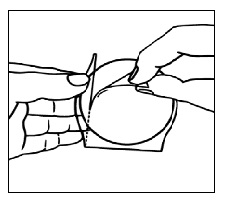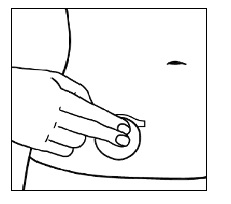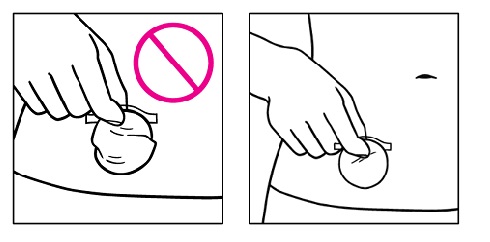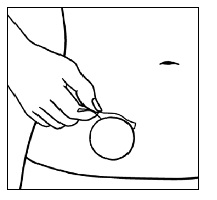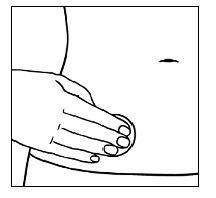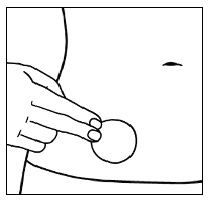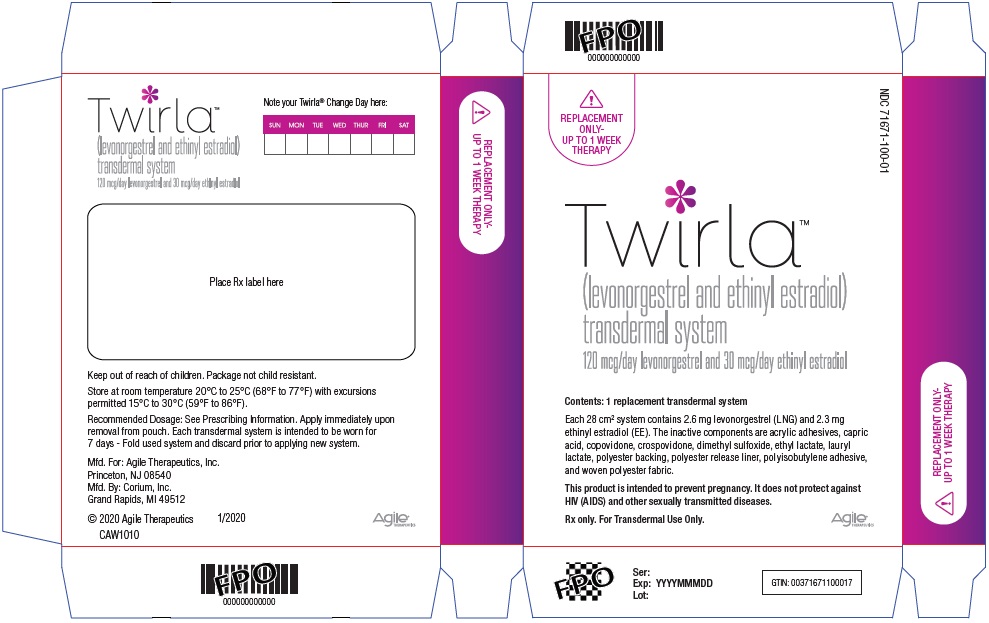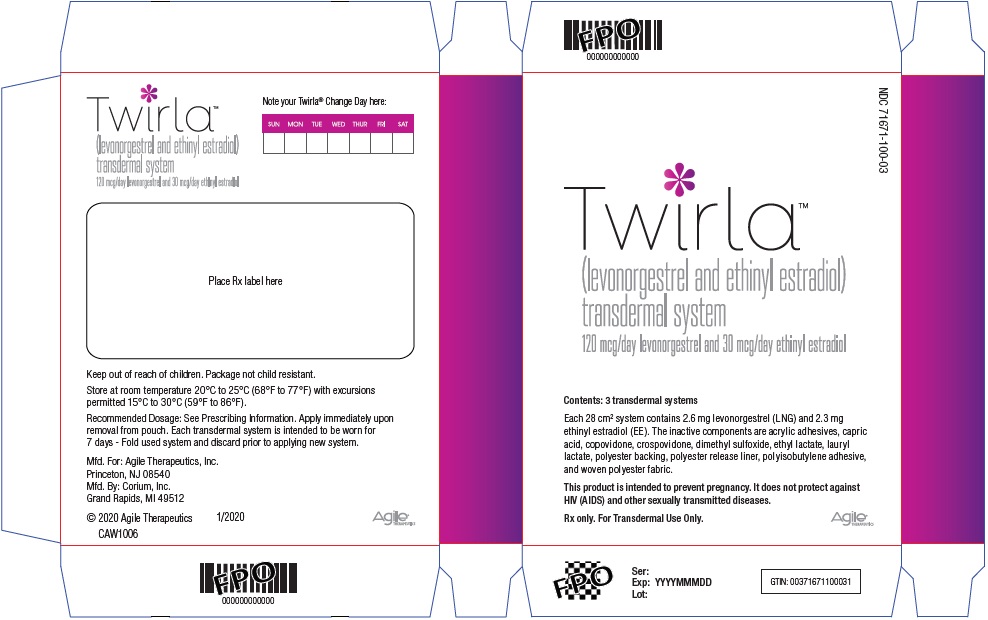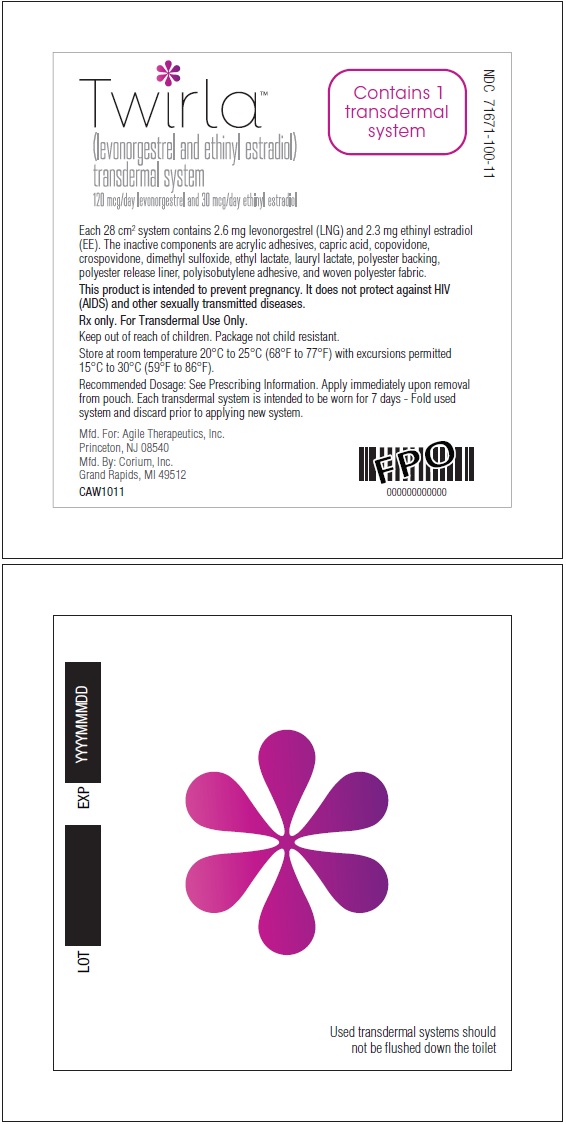 DRUG LABEL: Twirla
NDC: 71671-100 | Form: PATCH
Manufacturer: Agile Therapeutics, Inc.
Category: prescription | Type: HUMAN PRESCRIPTION DRUG LABEL
Date: 20240703

ACTIVE INGREDIENTS: LEVONORGESTREL 2.60 mg/1 1; ETHINYL ESTRADIOL 2.30 mg/1 1
INACTIVE INGREDIENTS: ETHYL LACTATE; CAPRIC ACID; DIMETHYL SULFOXIDE; LAURYL LACTATE; POLYISOBUTYLENE (55000 MW); POLYISOBUTYLENE (1100000 MW); COPOVIDONE K25-31; NITROGEN; HEPTANE; POLYBUTENE (1400 MW); CROSPOVIDONE (12 MPA.S AT 5%)

HIGHLIGHTS OF PRESCRIBING INFORMATION

These highlights do not include all the information needed to use TWIRLA® safely and effectively. See full prescribing information for TWIRLA.
TWIRLA (levonorgestrel and ethinyl estradiol) transdermal system
Initial U.S. Approval: 1968 (norgestrel and ethinyl estradiol)

WARNING: CIGARETTE SMOKING AND SERIOUS CARDIOVASCULAR EVENTS and CONTRAINDICATED IN WOMEN WITH A BMI ≥ 30 KG/M^2

See full prescribing information for complete boxed warning.

- TWIRLA is contraindicated in women over 35 years old who smoke. Cigarette smoking increases the risk of serious cardiovascular events from combination hormonal contraceptive (CHC) use. (4, 5.1)
- TWIRLA is contraindicated in women with a BMI ≥ 30 kg/m^2. Compared to women with a lower BMI, women with a BMI ≥ 30 kg/m^2 had reduced effectiveness and may have a higher risk for venous thromboembolic events. (4, 5.1, 8.9, 14)

RECENT MAJOR CHANGES

Warnings and Precautions (5.11) 04/2022

1 INDICATIONS AND USAGE

TWIRLA is a combination of levonorgestrel, a progestin, and ethinyl estradiol, an estrogen, indicated as a method of contraception for use in women of reproductive potential with a BMI < 30 kg/m^2 for whom a combined hormonal contraceptive is appropriate. (1)

Limitation of Use
Consider TWIRLA’s reduced effectiveness in women with a BMI ≥ 25 to < 30 kg/m^2 before prescribing. (4, 8.9, 14)

2 DOSAGE AND ADMINISTRATION

- For transdermal use only (2.2)
- Apply one TWIRLA transdermal system (TDS) every week for three consecutive weeks (2.1, 2.2)
- Apply TWIRLA to one of the following sites: abdomen, buttock or upper torso (excluding breasts) (2.2)
- Do not cut or alter the TDS in any way (2.2)

3 DOSAGE FORMS AND STRENGTHS

Transdermal system: 120 mcg/day levonorgestrel (LNG) and 30 mcg/day ethinyl estradiol (EE) (3)

4 CONTRAINDICATIONS

- High risk of arterial or venous thrombotic diseases (4)
- Breast cancer (4)
- BMI ≥ 30 kg/m^2 (4)
- Liver tumors, acute viral hepatitis or decompensated cirrhosis (4)
- Undiagnosed abnormal uterine bleeding (4)
- Pregnancy (4, 8.1)
- Hypersensitivity reactions to components of TWIRLA (4)
- Use of Hepatitis C drug combinations containing ombitasvir/paritaprevir/ritonavir, with or without dasabuvir (4)

5 WARNINGS AND PRECAUTIONS

- Vascular Risks: Stop TWIRLA if a thromboembolic event occurs. Stop TWIRLA at least 4 weeks before and through 2 weeks after major surgery. Start no earlier than 4 weeks after delivery, in women who are not breast-feeding. Consider cardiovascular risk factors before initiating in all women, particularly those over 35 years. (5.1, 5.5)
- Liver Disease: Discontinue TWIRLA if jaundice occurs. (5.2)
- Risk of Liver Enzyme Elevations with Concomitant Hepatitis C. (5.3)
- Hypertension: If used in women with well-controlled hypertension, monitor blood pressure and stop use if blood pressure rises significantly. (5.4)
- Gallbladder Disease: May cause or worsen gallbladder disease. (5.6)
- Adverse Carbohydrate and Lipid Metabolic Effect: Monitor glucose in prediabetic and diabetic women using TWIRLA. Consider an alternate contraceptive method for women with uncontrolled dyslipidemia. (5.7)
- Headache: Evaluate significant change in headaches and discontinue TWIRLA if indicated. (5.8)
- Uterine Bleeding: May cause irregular bleeding or amenorrhea. Evaluate for other causes if symptoms persist. (5.9)

6 ADVERSE REACTIONS

The most common adverse reactions (≥ 2%) in clinical trials for TWIRLA are application site disorders, nausea, headache, dysmenorrhea, and increased weight. (6.1)
To report SUSPECTED ADVERSE REACTIONS, contact Agile Therapeutics, Inc. at 1-888-389-4752 or FDA at 1-800-FDA-1088 or www.fda.gov/medwatch.

7 DRUG INTERACTIONS

Enzyme inducers (e.g., CYP3A4): May decrease the effectiveness of TWIRLA or increase breakthrough bleeding. Counsel women to use a back-up or alternative method of contraception when enzyme inducers are used with TWIRLA. (7.1)

8 USE IN SPECIFIC POPULATIONS

- Pregnancy: Discontinue if pregnancy occurs. (8.1)
- Lactation: Advise use of another method; TWIRLA can decrease milk production. (8.2)
- Body Mass Index: TWIRLA has demonstrated reduced effectiveness in women with BMI ≥ 25 kg/m^2 and women with a BMI ≥ 30 kg/m^2 may have a higher risk for VTEs with TWIRLA. (8.9)

FULL PRESCRIBING INFORMATION

WARNING: CIGARETTE SMOKING AND SERIOUS CARDIOVASCULAR EVENTS and CONTRAINDICATED IN WOMEN WITH A BMI ≥ 30 KG/M^2

Cigarette Smoking and Serious Cardiovascular Events
Cigarette smoking increases the risk of serious cardiovascular events from combined hormonal contraceptive (CHC) use. This risk increases with age, particularly in women over 35 years of age, and with the number of cigarettes smoked. For this reason, CHCs, including TWIRLA, are contraindicated in women who are over 35 years of age and smoke [see Contraindications (4) and Warnings and Precautions (5.1)].

Contraindicated in Women with a BMI ≥ 30 kg/m^2
TWIRLA is contraindicated in women with a BMI ≥ 30 kg/m^2. Compared to women with a lower BMI, women with a BMI ≥ 30 kg/m^2 had reduced effectiveness and may have a higher risk for venous thromboembolism events (VTEs) [see Contraindications (4) and Warnings and Precautions (5.1)].

1 INDICATIONS AND USAGE

TWIRLA is indicated as a method of contraception for use in women of reproductive potential with a BMI < 30 kg/m^2 for whom a combined hormonal contraceptive is appropriate.

Limitation of Use
Consider TWIRLA’s reduced effectiveness in women with a BMI ≥ 25 to < 30 kg/m^2 before prescribing TWIRLA [see Use in Specific Populations (8.9) and Clinical Studies (14)]. TWIRLA is contraindicated in women with a BMI ≥ 30 kg/m^2 [see Contraindications (4)].

2 DOSAGE AND ADMINISTRATION

2.1 How to Start Using TWIRLA

See the FDA-approved patient labeling (Instructions for Use).

The TWIRLA transdermal system (TDS) is used in a 28-day (four-week) cycle. A new TDS is applied and worn for seven days for three consecutive weeks (Weeks 1, 2, and 3). No TDS is worn during Week 4 (the TDS-Free Week), when withdrawal bleeding is expected.

On the day after Week 4 ends, a new 28-day cycle is started by applying a new TDS. Under no circumstances should there be more than a 7-day TDS-free interval between dosing cycles.

Breakthrough (Unscheduled) Bleeding or Spotting Occurrence
If unscheduled (breakthrough) spotting or bleeding occurs, instruct the woman to continue the same regimen. If the bleeding is persistent or prolonged consider causes other than TWIRLA. If the bleeding is persistent or prolonged, instruct the woman to consult with her healthcare provider.

In Case of Skin Irritation
If TDS use results in uncomfortable irritation, the TDS may be removed, and a new TDS may be applied to a different location until the next “Patch Change Day”. Only one TDS should be worn at a time.

Every new TDS should be applied on the same day of the week. This day is known as the “Patch Change Day.” For example, if the first TDS is applied on a Sunday, all subsequent TDS should be applied on a Sunday.

There are multiple options for starting the TDS, and the woman should choose the option that is most appropriate (see Table 1):

Table 1: Instructions for Administration
Starting TWIRLA in women with no current use of hormonal contraception | Day 1 Start; - The woman should apply the first TDS during the first 24 hours of menstruation. The woman should apply a new TDS each week for three weeks (21 total days). No TDS is worn during Week Four (the “Patch-Free Week”). - If a TDS is applied after the first 24 hours of menstruation, non-hormonal back-up contraception (such as condoms and spermicide, or diaphragm and spermicide) is needed for the first 7 days of the first cycle only.
Switching from another contraceptive method; - Oral combination hormonal contraception (oral CHC) | Start TWIRLA:; - The woman should complete the current pill cycle and apply the first TWIRLA TDS on the day the next pill cycle would normally start. - If menses does not occur within a week after taking the last active pill, instruct the woman to consult with a healthcare professional to be sure that pregnancy has not occurred. If no pregnancy has occurred, TWIRLA may be started for contraception. - If TWIRLA is applied more than a week after taking the last active pill, non-hormonal back-up contraception (such as condoms and spermicide, or diaphragm and spermicide) should be used concurrently for the first 7 days of TDS use.
- Transdermal system | - The woman should complete the current TDS cycle and apply the first TWIRLA TDS on the day the next TDS cycle would normally start. - If menses does not occur within a week after removing the last TDS, instruct the woman to consult with a healthcare professional to be sure that pregnancy has not occurred. If no pregnancy has occurred, TWIRLA may be started for contraception. - If TWIRLA is applied more than a week after removal of the last TDS, non-hormonal back-up contraception (such as condoms and spermicide, or diaphragm and spermicide) should be used concurrently for the first 7 days of TDS use.
- Vaginal ring | - The woman should complete the current vaginal ring cycle and apply the first TWIRLA TDS on the day the next vaginal ring would normally be inserted. - If menses does not occur within a week after removing the last vaginal ring, instruct the woman to consult with a healthcare professional to be sure that pregnancy has not occurred. If no pregnancy has occurred, TWIRLA may be started for contraception. - If TWIRLA is applied more than a week after removal of the last vaginal ring, non-hormonal back-up contraception (such as condoms and spermicide, or diaphragm and spermicide) should be used concurrently for the first 7 days of TDS use.
- Injection | - The woman should apply the first TDS on the day the next injection would normally occur.
- Intrauterine system (IUS) | - The woman should apply the first TDS on the day of IUS removal.
- Implant | - The woman should apply the first TDS on the day of implant removal.
- Progestin-only pill | - The woman should apply the first TDS on the day the next progestin-only pill cycle would normally start.

Use after an abortion or miscarriage:
TWIRLA may be started immediately for contraception within the first 5 days following a complete first trimester abortion or miscarriage without additional back-up contraception. If more than 5 days have elapsed from the first trimester abortion or miscarriage, then the woman should be advised to use non-hormonal contraception (such as condoms and spermicide, or diaphragm and spermicide) and follow instructions for starting TWIRLA for the first time. Ovulation may occur within 10 days of an abortion or miscarriage.

TWIRLA should not be started earlier than 4 weeks after a second trimester abortion or miscarriage due to the increased risk of thromboembolism [see Warnings and Precautions (5.1)].

Use of TWIRLA after childbirth:
For women who elect not to breastfeed, do not start TWIRLA sooner than 4 weeks after childbirth given the increased risk for thromboembolism [see Use in Specific Populations (8.2)].

If a woman begins using TWIRLA postpartum and has not yet had a period, consider the possibility of ovulation and pregnancy. If the woman is not pregnant, instruct her to use non-hormonal back-up contraception (such as condoms and spermicide, or diaphragm and spermicide) for the first 7 days of TDS use [see Warnings and Precautions (5.1) and Use in Specific Populations (8.1)].

2.2 Important Application Instructions

- See the FDA-approved patient labeling (Instructions for Use).
- TWIRLA TDS is applied once weekly for three weeks. Each TWIRLA TDS should be worn for one week. Instruct women to wear only one TWIRLA TDS at any time.
- To achieve maximum contraceptive effectiveness, TWIRLA must be used exactly as directed. The failure rate may increase when TDS application is delayed/missed or when TDS is applied incorrectly.
- Apply TWIRLA to clean, dry, and intact skin at the selected application site. Application sites include: the abdomen, buttock or upper torso (excluding the breasts). When applying a new TWIRLA TDS, do not apply the new TDS directly over the previous TDS site.
- Do not apply TWIRLA to skin that has been exposed to powder, oil, moisturizer, or lotion. Advise women not to routinely use large amounts of body lotions or oils at application sites.
- Prolonged exposure to water may interfere with adherence of TWIRLA.
- Do not cut or alter TWIRLA in any way, the whole TDS should be applied. If the TWIRLA TDS is cut or damaged or altered in size, contraceptive efficacy may be impaired.
- If the TWIRLA TDS lifts at the edges, reattach TWIRLA by pressing firmly and smoothing down the edges of the system. If TWIRLA comes off completely, reapply the TWIRLA TDS that detached.
- Discard TWIRLA by folding the used TDS so that the adhesive side sticks to itself and safely discard in the trash.

MANAGING PARTIAL OR COMPLETE TDS DETACHMENTS (see Table 2)
The TWIRLA TDS must adhere securely to the skin to work properly. Prolonged water exposure may compromise the TDS’s adherence. As a result, the woman should be instructed to check the TDS for partial or complete TDS detachment not only daily but also after prolonged water exposure.

If the TDS becomes partially or completely detached and remains detached, insufficient drug delivery may occur. Partial TDS detachment should be resolved since it can lead to the TDS getting caught on clothing and detaching. The woman should not try to reapply a TDS if it is no longer sticky, if it has become stuck to itself or another surface, and/or if it has other material stuck to it.

If a TDS edge lifts up:

- The woman should press down firmly on the TDS with the palm of the hand for 10 seconds, making sure that the whole TDS is adhered to her skin. Then run fingers over the entire surface area to smooth out any wrinkles around the edges of the TDS.
- If the lifted edge of the TDS does not stick completely after attempted re-adhesion, the TDS should be removed, and a new replacement TDS applied.
- Do not tape or wrap the TDS to the skin or reapply a TDS that is partially adhered to clothing.

If the TDS has been off or partially off:

- For less than one day, the woman should try to reapply it. If the TDS does not adhere completely, apply a new TDS immediately. No back-up contraception is needed and the “Patch Change Day” will stay the same.
- For more than one day OR if unsure of the timeframe, the woman may not be protected from pregnancy. To reduce this risk, apply a new TDS and start a new 4-week cycle. The woman will now have a new “Patch Change Day” and MUST USE NON-HORMONAL BACK-UP CONTRACEPTION (such as condoms and spermicide, or diaphragm and spermicide) for the first 7 days of the new cycle.

2.3 Missed Doses

Instruct women about the handling of missed doses (e.g., missed or delayed TDS application) and to follow the dosing instructions provided in the FDA-approved patient labeling.

FORGETTING TO CHANGE THE TDS:

- At the start of any TDS cycle (Week 1/Day 1): THE WOMAN MAY NOT BE PROTECTED FROM PREGNANCY. The woman should apply the first TDS of her new cycle as soon as she remembers, and this becomes the new "Patch Change Day" and a new "Day 1" of the cycle. The woman should use non-hormonal back-up contraception (such as condoms and spermicide, or diaphragm and spermicide) for the first 7 days of the new cycle.
- In the middle of the TDS cycle (Week 2/Day 8 or Week 3/Day 15), for 1 or 2 days (up to 48 hours): The woman should apply a new TDS immediately. The next TDS should be applied on the usual "Patch Change Day". No back-up contraception is needed.
- For more than 2 days (48 hours or more): THE WOMAN MAY NOT BE PROTECTED FROM PREGNANCY. The woman should stop the current contraceptive cycle and start a new four-week cycle immediately by putting on a new TDS. This is now a new "Patch Change Day" and a new "Day 1" of the cycle. Non-hormonal back-up contraception must be used for 7 days.
- At the end of the TDS cycle Week 3 (Day 22): If the woman forgets to remove her TDS, she should take it off as soon as she remembers. The next cycle should be started on the usual "Patch Change Day", which is the day after Day 28. No back-up contraception is needed.

Table 2: Managing Partial or Complete TDS Detachments and Late/Missed TDS Applications
Scenario | Results in New TDS- Change Day | Back-up Contraception Required (7 Days) | Starts New Cycle
Did not apply TDS on scheduled Day 1/Week 1 of new cycle (late TDS-on day) | Yes | Yes | Yes
TDS detached for < 24 hours | No | No | No
TDS detached for ≥ 24 hours, or unsure duration | Yes | Yes | Yes
< 48 hours late for Patch Change Day (Day 8 or 15) | No | No | No
≥ 48 hours late for Patch Change Day (Day 8 or 15) | Yes | Yes | Yes
Forgets to remove last TDS on Day 22 | No | No | No

Under no circumstances should there be more than a seven-day TDS-free interval between cycles. If there are more than 7 TDS-free days, THE WOMAN MAY NOT BE PROTECTED FROM PREGNANCY and non-hormonal back-up contraception (such as a condoms and spermicide, or diaphragm and spermicide) must be used for 7 days. As with CHCs, the risk of ovulation increases with each day beyond the recommended drug-free period. If the woman has intercourse during such an extended TDS-free interval, consider the possibility of pregnancy.

3 DOSAGE FORMS AND STRENGTHS

TWIRLA (120 mcg/day levonorgestrel and 30 mcg/day ethinyl estradiol) transdermal system is a circular beige colored product with the name and strength etched on the backing membrane.

4 CONTRAINDICATIONS

Twirla is contraindicated in females who are known to have or develop the following conditions:

- At high risk of arterial or venous thrombotic diseases. Examples include women who
  - Smoke, if over age 35 [see Boxed Warning and Warnings and Precautions (5.1)]
  - Have current or history of deep vein thrombosis or pulmonary embolism [see Warnings and Precautions (5.1)]
  - Have cerebrovascular disease [see Warnings and Precautions (5.1)]
  - Have coronary artery disease [see Warnings and Precautions (5.1)]
  - Have thrombogenic valvular or thrombogenic rhythm diseases of the heart (for example, subacute bacterial endocarditis with valvular disease, or atrial fibrillation) [see Warnings and Precautions (5.1)]
  - Have inherited or acquired hypercoagulopathies [see Warnings and Precautions (5.1)]
  - Have uncontrolled hypertension or hypertension with vascular disease [see Warnings and Precautions (5.4)]
  - Have diabetes mellitus and are over age 35, diabetes mellitus with hypertension or vascular disease or other end-organ damage, or diabetes mellitus of > 20 years duration [see Warnings and Precautions (5.7)]
- Have headaches with focal neurological symptoms, migraine headaches with aura
- Women over age 35 with any migraine headaches [see Warnings and Precautions (5.8)]
- BMI ≥ 30 kg/m^2. Compared to women with a lower BMI, women with a BMI ≥ 30 kg/m^2 had reduced effectiveness and may have a higher risk for VTEs [see Warnings and Precautions (5.1), Use in Specific Populations (8.9) and Clinical Studies (14)].
- Liver tumors (benign or malignant), acute viral hepatitis, or severe (decompensated) cirrhosis, or liver disease [see Warnings and Precautions (5.2)]
- Undiagnosed abnormal uterine bleeding [see Warnings and Precautions (5.9)]
- Pregnancy, because there is no reason to use CHCs during pregnancy [see Use in Specific Populations (8.1)]
- Current diagnosis of, or history of, breast cancer, which may be hormone-sensitive [see Warnings and Precautions (5.11)]
- Hypersensitivity to any components of TWIRLA. Observed reactions include itching and irritation at the TDS application site [see Adverse Reactions (6.1)]
- Use of Hepatitis C drug combinations containing ombitasvir/paritaprevir/ritonavir, with or without dasabuvir, due to the potential for alanine aminotransferase (ALT) elevations [see Warnings and Precautions (5.3)]

5 WARNINGS AND PRECAUTIONS

5.1 Thromboembolic Disorders and Other Vascular Conditions

Women are at increased risk for a venous thromboembolic event (VTE) when using CHCs, including TWIRLA. The risk of VTE may be greater in women with a BMI ≥ 30 kg/m^2 compared to women with a lower BMI, and TWIRLA is contraindicated in obese patients [see Contraindications (4)]. In the Phase 3 clinical trial, four TWIRLA-treated women experienced a VTE. All of these women had a BMI > 30 kg/m^2 [see Adverse Reactions (6.1)].

- Stop TWIRLA if an arterial or venous thromboembolic event occurs.
- Stop TWIRLA if there is unexplained loss of vision, proptosis, diplopia, papilledema, or retinal vascular lesions. Evaluate for retinal vein thrombosis immediately.
- Discontinue TWIRLA during prolonged immobilization and resume treatment based on clinical judgement. If feasible, stop TWIRLA at least 4 weeks before and through 2 weeks after major surgery or other surgeries known to have an elevated risk of thromboembolism.
- Start TWIRLA no earlier than four weeks after delivery in women who are not breast-feeding. The risk of postpartum thromboembolism decreases after the third postpartum week, whereas the likelihood of ovulation increases after the third postpartum week.
- Before starting TWIRLA, evaluate any past medical history or family history of thromboembolism or thromboembolic disorders. Consider whether the history suggests an inherited or acquired hypercoagulopathy. TWIRLA is contraindicated in women with a high risk of arterial or venous thromboembolic diseases [see Contraindications (4)].

Arterial Events
CHCs increase the risk of cardiovascular events and cerebrovascular events, such as myocardial infarction and stroke. The risk is greater among older women (> 35 years of age), smokers, and women with hypertension, dyslipidemia, diabetes, or obesity.

TWIRLA is contraindicated in women over 35 years of age who smoke [see Contraindications (4)]. Cigarette smoking increases the risk of serious cardiovascular events from CHC use. This risk increases with age, particularly in women over 35 years of age, and with the number of cigarettes smoked.

Venous Events
The use of CHCs increases the risk of VTEs, such as deep vein thrombosis and pulmonary embolism. Risk factors for VTEs include smoking, obesity, and family history of VTE, in addition to other factors that contraindicate use of CHCs. While the increased risk of VTE associated with the use of CHCs is well-established, the rates of VTE are even greater during pregnancy, especially during the postpartum period (see Figure 1). The rate of VTE in women using CHCs has been estimated to be 3 to 12 cases per 10,000 woman-years for non-oral CHCs.

The risk of VTE is highest during the first year of use of a combined oral contraceptive (COC) and when restarting hormonal contraception after a break of four weeks or longer. This initial higher risk declines during the first year, but users of CHCs remain at an increased risk of VTE compared to non-users of CHCs. Based on results from a few studies, there is some evidence that this is true for non-oral products as well. The risk of thromboembolic disease due to CHCs gradually disappears after CHC use is discontinued.

Figure 1 shows the risk of developing a VTE for women who are not pregnant and do not use hormonal contraceptives, for women who use hormonal contraceptives with a range of doses and routes of administration, for pregnant women, and for women in the postpartum period. To put the risk of developing a VTE into perspective: If 10,000 women who are not pregnant and do not use hormonal contraceptives are followed for one year, between 1 and 5 of these women will develop a VTE.

Figure 1. Likelihood of Developing a VTE Within One Year Among Pregnant and Non-Pregnant Women

*CHC = combination hormonal contraception
** Pregnancy data based on actual duration of pregnancy in the reference studies. Based on a model assumption that pregnancy duration is 9 months, the rate is 7 to 27 per 10,000 WY.

5.2 Liver Disease

Elevated Liver Enzymes
TWIRLA is contraindicated in women with acute viral hepatitis or severe (decompensated) cirrhosis of the liver [see Contraindications (4)]. Discontinue TWIRLA if jaundice develops. Acute liver test abnormalities may necessitate the discontinuation of CHC use until the liver tests return to normal and CHC causation has been excluded.

Liver Tumors
TWIRLA is contraindicated in women with benign or malignant liver tumors [see Contraindications (4)]. CHCs increase the risk of hepatic adenomas. An estimate of the attributable risk is 3.3 cases/100,000 CHC users. Rupture of hepatic adenomas may cause death from abdominal hemorrhage.

Studies have shown an increased risk of developing hepatocellular carcinoma in long-term (> 8 years) CHC users. The attributable risk of liver cancers in CHC users is less than one case per million users.

5.3 Risk of Liver Enzyme Elevations with Concomitant Hepatitis C Treatment

During clinical trials with the Hepatitis C combination drug regimen that contains ombitasvir/paritaprevir/ritonavir, with or without dasabuvir, ALT elevations greater than 5 times the upper limit of normal (ULN), including some cases greater than 20 times the ULN, were significantly more frequent in women using ethinyl estradiol-containing medications, such as CHCs. CHCs, such as TWIRLA, are contraindicated for use with Hepatitis C drug combinations containing ombitasvir/paritaprevir/ritonavir, with or without dasabuvir [see Contraindications (4)]. Discontinue TWIRLA prior to starting therapy with the combination drug regimen ombitasvir/paritaprevir/ritonavir, with or without dasabuvir. TWIRLA can be restarted approximately 2 weeks following completion of treatment with the Hepatitis C combination drug regimen.

5.4 Hypertension

TWIRLA is contraindicated in women with uncontrolled hypertension or hypertension with vascular disease [see Contraindications (4)]. For all women, including those with well-controlled hypertension, monitor blood pressure at routine visits and stop TWIRLA if blood pressure rises significantly.

An increase in blood pressure has been reported in women using CHCs, and this increase is more likely in older women with extended duration of use. The effect of CHCs on blood pressure may vary according to the progestin in the CHC.

5.5 Age-Related Considerations

The risk for cardiovascular disease and prevalence of risk factors for cardiovascular disease increase with age. Certain conditions, such as smoking and migraine headache without aura, that do not contraindicate CHC use in younger women, are contraindications to use in women over 35 years of age [see Contraindications (4) and Warnings and Precautions (5.1)]. Consider the presence of underlying risk factors that may increase the risk of cardiovascular disease or VTE, particularly before initiating a CHC for women over 35 years, such as:

- Hypertension
- Diabetes
- Dyslipidemia
- Obesity

5.6 Gallbladder Disease

Studies suggest an increased risk of developing gallbladder disease among CHC users. Use of CHCs may also worsen existing gallbladder disease.

A past history of CHC-related cholestasis predicts an increased risk with subsequent CHC use. Women with a history of pregnancy-related cholestasis may be at an increased risk for CHC-related cholestasis.

5.7 Adverse Carbohydrate and Lipid Metabolic Effects

Hyperglycemia
TWIRLA is contraindicated in diabetic women over age 35, or women who have diabetes with hypertension, nephropathy, retinopathy, neuropathy, other vascular disease, or women with diabetes of > 20 years duration [see Contraindications (4)]. TWIRLA may decrease glucose tolerance. Carefully monitor prediabetic and diabetic women who are using TWIRLA.

Dyslipidemia
Consider alternative contraception for women with uncontrolled dyslipidemia. TWIRLA may cause adverse lipid changes.

Women with hypertriglyceridemia, or a family history thereof, may have an increase in serum triglyceride concentrations when using TWIRLA, which may increase the risk of pancreatitis.

5.8 Headache

TWIRLA is contraindicated in women who have headaches with focal neurological symptoms or have migraine headaches with aura, and in women over age 35 years who have migraine headaches with or without aura [see Contraindications (4)].

If a woman using TWIRLA develops new headaches that are recurrent, persistent, or severe, evaluate the cause and discontinue TWIRLA if indicated. Consider discontinuation of TWIRLA if there is any increased frequency or severity of migraines during CHC use (which may be prodromal of a cerebrovascular event).

5.9 Bleeding Irregularities and Amenorrhea

Unscheduled and Scheduled Bleeding and Spotting
Women using TWIRLA may experience unscheduled (breakthrough or intracyclic) bleeding and spotting, especially during the first three months of use. Bleeding irregularities may resolve over time or by changing to a different contraceptive product. If bleeding persists or occurs after previously regular cycles on TWIRLA, evaluate for causes such as pregnancy or malignancy.

Based on women’s electronic diaries from a clinical trial evaluating the safety and efficacy of TWIRLA, the proportion of subjects reporting unscheduled bleeding per 28-day cycle decreased over time. At cycle 1 and 2, 60.4% and 52.6%, respectively reported unscheduled bleeding and/or spotting. At cycle 13, 42.3% of women reported unscheduled bleeding and/or spotting. Women reported a mean number of unscheduled bleeding/spotting days per month that generally decreased over the 13 cycles and was a mean of 1.6 days in Cycle 13. A total of 45 women (2.2%) discontinued the study prematurely due to menstrual disorders including metrorrhagia, vaginal hemorrhage, menorrhagia, dysmenorrhea, irregular menstruation, dysfunctional uterine bleeding, and menstrual disorder [see Clinical Trial Experience (6.1) and Clinical Studies (14)].

Amenorrhea and Oligomenorrhea
Women who use TWIRLA may experience absence of scheduled (withdrawal) bleeding, even if they are not pregnant. Based on electronic patient diaries from the clinical trial, the percentages of women with no bleeding and/or spotting days (amenorrhea) in a cycle ranged from 6.3% to 11.9% over 13 cycles [see Clinical Trial Experience (6.1) and Clinical Studies (14)].

If scheduled bleeding does not occur, consider the possibility of pregnancy. If the woman has not adhered to the prescribed dosing schedule (missed days of active therapy or started her TDS on a day later than she should have), consider the possibility of pregnancy at the time of the first missed period and perform appropriate diagnostic measures. If the woman has adhered to the prescribed dosing schedule and misses two consecutive periods, rule out pregnancy.

After discontinuation of TWIRLA, amenorrhea or oligomenorrhea may occur, especially if these conditions were pre-existent.

5.10 Depression

Carefully observe women with a history of depression and discontinue TWIRLA if depression recurs to a serious degree. Data on the association of CHCs with onset of depression or exacerbation of existing depression are limited.

5.11 Malignant Neoplasms

Breast Cancer
Twirla is contraindicated in females who currently have or have had breast cancer because breast cancer may be hormonally sensitive [see Contraindications (4)].

Epidemiology studies have not found a consistent association between use of COCs and breast cancer risk. Studies do not show an association between ever (current or past) use of COCs and risk of breast cancer. However, some studies report a small increase in the risk of breast cancer among current or recent users (<6 months since last use) and current users with longer duration of COC use [see Postmarketing Experience (6.2)].

Cervical Cancer
Some studies suggest that CHCs are associated with an increase in the risk of cervical cancer or intraepithelial neoplasia. There is controversy about the extent to which these findings are due to differences in sexual behavior and other factors.

5.12 Effect on Binding Globulins

The estrogen component of TWIRLA may raise the serum concentrations of thyroxine-binding globulin, sex hormone-binding globulin, and cortisol-binding globulin. The dose of replacement thyroid hormone or cortisol therapy may need to be increased.

5.13 Hereditary Angioedema

In women with hereditary angioedema, exogenous estrogens may induce or exacerbate symptoms of angioedema.

5.14 Chloasma

Chloasma may occur with TWIRLA use, especially in women with a history of chloasma gravidarum. Advise women with a history of chloasma to avoid exposure to the sun or ultraviolet radiation while using TWIRLA.

6 ADVERSE REACTIONS

The following serious adverse reactions with the use of CHCs, including TWIRLA, are discussed elsewhere in the labeling:

- Thromboembolic Disorders and Other Vascular Conditions [see Warnings and Precautions (5.1)]
- Liver disease [see Warnings and Precautions (5.3)]

6.1 Clinical Trial Experience

Because clinical trials are conducted under widely varying conditions, adverse reaction rates observed in the clinical trials of one product cannot be directly compared to rates in the clinical trials of another product and may not reflect the rates observed in practice.

The safety of TWIRLA was evaluated in a 12-month, multicenter, open-label, single-arm clinical trial (NCT02158572) conducted in the United States [see Clinical Studies (14)]. Women applied TWIRLA (120 mcg LNG/30 mcg EE) for 13 28-day treatment cycles. One treatment cycle is defined as three consecutive weeks that one TWIRLA TDS is applied for seven-day wear followed by one week that TWIRLA is not applied.

The safety population for this clinical trial was composed of 2,031 women that contributed 18,841 treatment cycles of exposure. Of these 2,031 women, 989 women completed 13 treatment cycles. The mean age was 27.5 years. The mean BMI for the safety population was 28.3 kg/m^2. The BMI of the safety population was widely distributed: 39.4% had a BMI < 25 kg/m^2, 25.3% had a BMI ≥ 25 kg/m^2 and < 30 kg/m^2, and 35.3% had a BMI ≥ 30 kg/m^2.

For women who received TWIRLA, the most common reasons for discontinuation from the study were a womans decision (15.3%) and lost to follow-up (11.3%).

Discontinuation due to an adverse reaction occurred in 10.9% of women. The most common (≥ 2%) adverse reactions leading to discontinuation were application site disorder (3.1%) and any bleeding irregularities (2.2%).

The most common adverse reactions that occurred in ≥ 2% of the 2,031 women that used TWIRLA are shown in Table 3.

Table 3: Adverse Drug Reactions Reported by 2% of TWIRLA-Treated Women in One Phase 3 Clinical Trial
Adverse reaction | TWIRLA (n=2,031)
General disorders and administration site conditions Application site disorder [Represents a bundle of similar terms that include the following adverse reactions: application site acne, hemorrhage, pustules, dermatitis, hypersensitivity, rash, discoloration, induration, reaction, dryness, irritation, ulcer, erosion, pain, urticaria, erythema, papules, vesicles, exfoliation, pruritis.] | 6.2%
Gastrointestinal disorders Nausea | 4.1%
Nervous system disorders Headache | 3.6%
Reproductive system and breast disorder Dysmenorrhoea | 2.3%
Investigations Weight increased | 2.0%

Venous Thromboembolic Events (VTEs)

A total of four VTEs (including pulmonary embolism and deep vein thrombosis) in TWIRLA-treated patients were identified in the clinical trial. Of these, all were in women with a BMI > 30 kg/m^2 [see Contraindications (4)].

Other Serious Adverse Reactions
The following serious adverse reactions occurred in < 1% of women who received TWIRLA: cholelithiasis, cholecystitis, major depression, suicidal ideation, appendicitis, ectopic pregnancy, pneumonia, and gastroenteritis.

6.2 Postmarketing Experience

Five studies that compared breast cancer risk between ever-users (current or past use) of combined oral contraceptives (COCs) and never-users of COCs reported no association between ever use of COCs and breast cancer risk, with effect estimates ranging from 0.90 - 1.12 (Figure 2).

Three studies compared breast cancer risk between current or recent COC users (<6 months since last use) and never users of COCs (Figure 2). One of these studies reported no association between breast cancer risk and COC use. The other two studies found an increased relative risk of 1.19 - 1.33 with current or recent use. Both of these studies found an increased risk of breast cancer with current use of longer duration, with relative risks ranging from 1.03 with less than one year of COC use to approximately 1.4 with more than 8-10 years of COC use.

Figure 2. Relevant Studies of Risk of Breast Cancer with Combined Oral Contraceptives

RR = relative risk; OR = odds ratio; HR = hazard ratio. “ever COC” are females with current or past COC use; “never COC use” are females that never used COCs.

7 DRUG INTERACTIONS

The sections below provide information on substances for which data on drug interactions with CHCs are available. There is little information available about the clinical effect of most drug interactions that may affect CHCs. However, based on the known pharmacokinetic effects of these drugs, clinical strategies to minimize any potential adverse effect on contraceptive effectiveness or safety are suggested.

Consult the approved product labeling of all concurrently used drugs to obtain further information about interactions with CHCs or the potential for metabolic enzyme or transporter system alterations.

No drug-drug interaction studies were conducted with TWIRLA.

7.1 Effects of Other Drugs on Combined Hormonal Contraceptives

Substances Decreasing Plasma Concentration of CHCs and Potentially Diminishing the Efficacy of CHCs:

Table 4 includes substances that demonstrated an important drug interaction with TWIRLA.

Table 4: Significant Drug Interactions Involving Substances That Affect CHCs
Metabolic Enzyme Inducers
Clinical effect | - Concomitant use of CHCs with metabolic enzyme inducers may decrease the plasma concentrations of the estrogen and/or progestin component of CHCs [see Clinical Pharmacology (12.3)]. - Decreased exposure of the estrogen and/or progestin component of CHCs may potentially diminish the effectiveness of CHCs and may lead to contraceptive failure or an increase in breakthrough bleeding.
Prevention or management | - Counsel women to use an alternative method of contraception or a backup method when enzyme inducers are used with CHCs. - Continue backup contraception for 28 days after discontinuing the enzyme inducer to maintain contraceptive reliability.
Examples | - Aprepitant, barbiturates, bosentan, carbamazepine, efavirenz, felbamate, griseofulvin, oxcarbazepine, phenytoin, rifampin, rifabutin, rufinamide, topiramate, products containing St. John’s wort, [Induction potency of St. John’s wort may vary widely based on preparation.] and certain protease inhibitors (see separate section on protease inhibitors below).
Colesevelam
Clinical effect | - Concomitant use of CHCs with Colesevelam significantly decreases systemic exposure of ethinyl estradiol [see Clinical Pharmacology (12.3)]. - Decreased exposure of the estrogen component of CHCs may potentially reduce contraceptive efficacy or result in an increase in breakthrough bleeding, depending on the strength of ethinyl estradiol in the CHC.
Prevention or management | Administer 4 or more hours apart to attenuate this drug interaction.

Substances increasing the systemic exposure of CHCs:
Co-administration of atorvastatin or rosuvastatin and CHCs containing ethinyl estradiol increase systemic exposure of ethinyl estradiol by approximately 20 to 25 percent. Ascorbic acid and acetaminophen may increase systemic exposure of ethinyl estradiol, possibly by inhibition of conjugation. CYP3A4 inhibitors such as itraconazole, voriconazole, fluconazole, grapefruit juice, or ketoconazole may increase systemic exposure of the estrogen and/or progestin component of CHCs.

Human immunodeficiency virus (HIV)/hepatitis C virus (HCV) protease inhibitors and non-nucleoside reverse transcriptase inhibitors:
Significant decreases in systemic exposure of the estrogen and/or progestin have been noted when CHCs are co-administered with some HIV protease inhibitors (e.g., nelfinavir, ritonavir, darunavir/ritonavir, (fos)amprenavir/ritonavir, lopinavir/ritonavir, and tipranavir/ritonavir), some HCV protease inhibitors (e.g., boceprevir and telaprevir), and some non-nucleoside reverse transcriptase inhibitors (e.g., nevirapine).

In contrast, significant increases in systemic exposure of the estrogen and/or progestin have been noted when CHCs are co-administered with certain other HIV protease inhibitors (e.g., indinavir and atazanavir/ritonavir) and with other non-nucleoside reverse transcriptase inhibitors (e.g., etravirine).

7.2 Effects of Combined Hormonal Contraceptives on Other Drugs

Table 5 provides significant drug interaction information for drugs co-administered with TWIRLA.

Table 5: Significant Drug Interaction Information for Drugs Co-Administered with CHCs
Lamotrigine
Clinical effect | - Concomitant use of CHCs with lamotrigine may significantly decrease systemic exposure of lamotrigine due to induction of lamotrigine glucuronidation [see Clinical Pharmacology (12.3)]. - Decreased systemic exposure of lamotrigine may reduce seizure control.
Prevention or management | Dose adjustment may be necessary. Consult the approved product labeling for lamotrigine.
Thyroid Hormone Replacement Therapy or Corticosteroid Replacement Therapy
Clinical effect | Concomitant use of CHCs with thyroid hormone replacement therapy or corticosteroid replacement therapy may increase systemic exposure of thyroid-binding and cortisol-binding globulin [see Warnings and Precautions (5.12)].
Prevention or management | The dose of replacement thyroid hormone or cortisol therapy may need to be increased. Consult the approved product labeling for the therapy in use. [see Warnings and Precautions (5.12)].
Other Drugs
Clinical effect | Concomitant use of CHCs may decrease systemic exposure of acetaminophen, morphine, salicylic acid, and temazepam. Concomitant use with ethinyl estradiol-containing CHCs may increase systemic exposure of other drugs (e.g., cyclosporine, prednisolone, theophylline, tizanidine, and voriconazole).
Prevention or management | The dosage of drugs that can be affected by this interaction may need to be increased. Consult the approved product labeling for the concomitantly used drug.

7.3 Effect on Laboratory Tests

The use of CHCs may influence the results of some laboratory tests, such as coagulation factors, lipids, glucose tolerance, and binding proteins.

7.4 Concomitant Use with HCV Combination Therapy – Liver Enzyme Elevation

CHCs are contraindicated for use with Hepatitis C drug combinations containing ombitasvir/paritaprevir/ritonavir, with or without dasabuvir [see Warnings and Precautions (5.4) and Contraindications (4)]. Discontinue TWIRLA prior to starting therapy with the combination drug regimen ombitasvir/paritaprevir/ritonavir, with or without dasabuvir. TWIRLA can be restarted approximately 2 weeks following completion of treatment with the Hepatitis C combination drug regimen.

8 USE IN SPECIFIC POPULATIONS

8.1 Pregnancy

Risk Summary
TWIRLA is contraindicated in pregnancy because there is no reason to use CHCs in pregnancy. Discontinue TWIRLA if pregnancy occurs. Epidemiologic studies and meta-analyses have not found an increased risk of genital or non-genital birth defects (including cardiac anomalies and limb-reduction defects) following exposure to CHCs before conception or during early pregnancy.

In the U.S. general population, the estimated background risk of major birth defects and miscarriage in clinically recognized pregnancies is 2–4% and 15–20%, respectively.

8.2 Lactation

Risk Summary
Contraceptive hormones and/or metabolites are present in human milk. CHCs can reduce milk production in breastfeeding women. This reduction can occur at any time but is less likely to occur once breastfeeding is well established. Advise the nursing woman to use another method of contraception until she discontinues breastfeeding [see Dosage and Administration (2.1)].

Human Data
No studies have been conducted on the use of TWIRLA in breastfeeding women.

8.4 Pediatric Use

The safety and effectiveness of TWIRLA as a method of contraception have been established in females of reproductive potential with a BMI < 30 kg/m^2. Efficacy is expected to be the same in postmenarcheal females regardless of age. TWIRLA is not indicated in females before menarche.

8.5 Geriatric Use

TWIRLA has not been studied in postmenopausal women and is not indicated in this population.

8.6 Hepatic Impairment

No studies have been conducted to evaluate the effect of hepatic impairment on the disposition of TWIRLA. However, steroid hormones may be poorly metabolized in patients with impaired liver function. Acute or chronic disturbances of liver function may necessitate the discontinuation of CHC use until markers of liver function return to normal and CHC causation has been excluded [see Contraindications (4) and Warnings and Precautions (5.2)].

8.9 Body Mass Index (BMI)

Compared to women with a lower BMI, women with a BMI ≥ 30 kg/m^2 had reduced effectiveness and may have a higher risk for VTEs. Therefore, TWIRLA is contraindicated in women with a BMI ≥ 30 kg/m^2 [see Contraindications (4) and Clinical Studies (14)].

TWIRLA has demonstrated reduced efficacy in women with a BMI ≥ 25 and < 30 kg/m^2 [see Clinical Studies (14)]. Consider this before prescribing TWIRLA to women with a BMI ≥ 25 to < 30 kg/m^2.

10 OVERDOSAGE

There have been no reports of serious adverse outcomes from overdose of CHCs, including ingestion by children. Overdose may cause uterine bleeding in women and nausea. In case of suspected overdose, the TWIRLA TDS should be removed and symptomatic treatment given.

11 DESCRIPTION

TWIRLA (levonorgestrel and ethinyl estradiol) transdermal system (TDS) contains 2.60 mg levonorgestrel (LNG) (17α)-(–) [13-ethyl-17¬hydroxy-18, 19-dinorpregn-4-en-20-yn-3-one], a progestin, and 2.30 mg ethinyl estradiol (EE), [(17α)-19-norpregna-1, 3, 5(10)-trien-20-yne-3, 17-diol] an estrogen (Figure 3).

Figure 3. Structural Formulas

TWIRLA is designed to provide daily exposure of 120 mcg LNG and 30 mcg EE. TWIRLA is a matrix type TDS consisting of a 15 cm^2 active adhesive laminate center, surrounded by a peripheral inactive adhesive laminate. The entire area of TWIRLA is 28 cm^2.

TWIRLA consists of 5 layers and a release liner which is removed and discarded prior to application. The two innermost layers contain the active ingredients (LNG and EE), as well as inactive components. Proceeding from the outer surface toward the surface adhering to the skin, the layers are (1) a woven peripheral backing layer, which is etched with “TWIRLA Levonorgestrel 120 mcg/day Ethinyl Estradiol 30 mcg/day”; (2) an inactive peripheral acrylic adhesive layer; (3) an inactive peripheral polyisobutylene adhesive layer; (4) an internal membrane to separate the active adhesive matrix from the inactive adhesive laminate; (5) the active adhesive matrix (Figure 4).

Figure 4. Schematic Depiction of the TWIRLA TDS

The inactive components are acrylic adhesives, capric acid, copovidone, crospovidone, dimethyl sulfoxide, ethyl lactate, lauryl lactate, polybutene, polyester internal membrane, polyester release liner, polyisobutylene adhesives, and woven polyester backing membrane. TWIRLA is not made with latex.

12 CLINICAL PHARMACOLOGY

12.1 Mechanism of Action

Combination hormonal contraceptives lower the risk of becoming pregnant primarily by suppressing ovulation.

12.2 Pharmacodynamics

TWIRLA exhibited ovulation inhibition as defined by serum progesterone concentrations. In one study subjects were treated with TWIRLA for three cycles. In this study, approximately 80% of these subjects had serum progesterone concentrations < 4.7 ng/mL.

12.3 Pharmacokinetics

TWIRLA is a TDS designed with an active matrix core containing LNG and EE. TWIRLA delivers medication to the systemic circulation by absorption of LNG and EE through the skin.

Absorption
Following application of TWIRLA, both LNG and EE reach a plateau by 24 to 48 hours (Figures 5 and 6). Delivery of hormones is continuous over the 7 days of TWIRLA wear. The mean pharmacokinetic parameters (Css and AUC0‑168) for LNG and EE following two consecutive cycles of TWIRLA are summarized in Table 6.

Table 6: Mean (%CV [Coefficient of Variation]) Pharmacokinetic Parameters of Levonorgestrel and Ethinyl Estradiol Following Two Consecutive Cycles of TWIRLA Wear on the Buttock
NC: not calculable
Analyte | Parameter | Cycle 1 Week 1 (N=18) | Cycle 1 Week 3 (N=18) | Cycle 2 Week 1 (N=18) | Cycle 2 Week 3 (N=18)
LNG | Css (pg/mL) [Average concentration within the 48-168 h time interval] | 842 (41.2) | 2009 (47.2) | 1389 (46.5) | 2209 (44.5)
LNG | AUC0-168 (ng∙h/mL) [AUC0-168: area under the plasma drug concentration-time curve calculated between 0 and 168 h] | 120.0 (39.1) | 339.0 (41.1) | 207.0 (44.1) | 378.0 (43.8)
LNG | t1/2 (h) [t1/2: elimination half-life] | NC | 38.2 (22.7) | NC | 40.5 (15.4)
EE | Css (pg/mL) | 31.9 (37.4) | 34.8 (37.4) | 38.6 (41.7) | 40.3 (38.9)
EE | AUC0-168 (pg∙h/mL) | 5040 (35.4) | 6210 (34.2) | 6060 (35.9) | 7120 (36.6)
EE | t1/2 (h) | NC | 19.7 (18.8) | NC | 20.5 (18.2)

In multiple dose studies, AUC0-168 for LNG and EE showed within-cycle and between cycle increases and the mean serum concentrations of EE and LNG were highest during the third Week of Cycle 2 after two consecutive cycles of wear (Figures 5 and 6). In a three-cycle study, the steady-state pharmacokinetics of EE and LNG was reached during Cycle 2. Upon removal of TWIRLA, serum levels of EE and LNG reach non‑measurable levels and low levels within 3 days, respectively.

Figure 5. Mean Serum Ethinyl Estradiol Concentrations in Healthy Female Volunteers Following Two Consecutive Cycles of TWIRLA Wear on the Buttock (Vertical arrow indicates time of TWIRLA removal)

Figure 6. Mean Serum Levonorgestrel Concentrations in Healthy Female Volunteers Following Two Consecutive Cycles of TWIRLA Wear on the Buttock (Vertical arrow indicates time of TWIRLA removal)

The absorption of LNG and EE following application of TWIRLA to the buttock, abdomen, and upper torso (excluding the breasts) was examined. While absorption from the abdomen was slightly lower than from other sites, absorption from all three anatomic sites was considered to be therapeutically equivalent.

The absorption of LNG and EE following application of TWIRLA was studied under various external conditions including sauna, whirlpool, treadmill, and in a cold-water bath. Somewhat lower drug concentration levels were reported for whirlpool and treadmill with geometric ratios within the 78-90% range for both LNG and EE and dry sauna (LNG only).

Distribution
LNG in serum is primarily bound to sex hormone-binding globulin (SHBG). EE is about 97% bound to plasma albumin. EE does not bind to SHBG but induces SHBG synthesis.

Elimination
Metabolism
Since TWIRLA is applied transdermally, first-pass metabolism (via the gastrointestinal tract and/or liver) of LNG and EE that would be expected with oral administration does not occur. Hepatic metabolism of LNG and EE occurs as described below.

Levonorgestrel: The most important metabolic pathways are reduction of the Δ4-3-oxo group and hydroxylation at positions 2α, 1β, and 16β, followed by conjugation. Most of the circulating metabolites are sulfates of 3α, 5β-tetrahydro-levonorgestrel, while excretion occurs predominantly in the form of glucuronides. Some of the parent LNG also circulates as 17β-sulfate. Metabolic clearance rates may differ among individuals by several-fold, and this may account in part for the wide variation observed in LNG concentrations among users.

Ethinyl estradiol: Cytochrome P450 enzymes (CYP3A4) in the liver are responsible for the 2-hydroxylation that is the major oxidative reaction. The 2-hydroxy metabolite is further transformed by methylation and glucuronidation prior to urinary and fecal excretion. Levels of CYP3A4 vary widely among individuals and can explain the variation in rates of EE 2-hydroxylation.

Excretion
LNG and its metabolites are excreted in the urine (40% to 68%) and in feces (16% to 48%). The mean terminal elimination half-life for LNG in TWIRLA is approximately 41 ± 6.2 hours at steady state.

EE is excreted in the urine and feces as glucuronide and sulfate conjugates and undergoes enterohepatic recirculation. The terminal elimination half-life of EE in TWIRLA is approximately 21 ± 3.7 hours at steady state.

13 NONCLINICAL TOXICOLOGY

13.1 Carcinogenesis, Mutagenesis, Impairment of Fertility

[see Warnings and Precautions (5.11) and Use in Specific Populations (8.1)]

14 CLINICAL STUDIES

The efficacy of TWIRLA was evaluated in one open label, single arm, multicenter trial in the United States (Study 1) (NCT02158572) of one-year duration that enrolled 2,031 women, ranging in age between 18 and 60 years, who were healthy and sexually active with regular menstrual cycles. For the primary efficacy analysis, 1,736 women between the ages 18 and 35 years completed 15,165 evaluable 28-day cycles with TWIRLA, where no back-up contraception was used, and sexual intercourse occurred.

The racial/ethnic distribution for the primary analysis was White (67%), Black/African American (24%), Asian (4%), American Indian/Alaskan Native (0.5%), Native Hawaiian/Pacific Islander (0.5%), Other/Multiple races (5%); 19% of the study population were Hispanic. The mean age was 26 years.

The mean BMI in the primary efficacy analysis group was 28.3 kg/m^2, and 35.3% of subjects had a BMI 30 kg/m^2. The primary efficacy endpoint was the Pearl Index (PI) defined as the pregnancy rate per 100 woman-years of use. The overall PI for the primary analysis population (TWIRLA-treated patients) was 5.8 (95% CI 4.5, 7.2). There were clear differences in efficacy by BMI category as shown in Table 7 below.

Table 7: Pearl Index Efficacy Analysis in TWIRLA-Treated Patients by BMI Subgroup in Study 1 [TWIRLA is contraindicated in women with a BMI ≥ 30 kg/m^2]
BMI | Number of evaluable cycles | Pearl Index (95% CI)
< 25 kg/m^2 | 6007 | 3.5 (1.8 - 5.2)
≥ 25 and < 30 kg/m^2 | 3881 | 5.7 (3.0 - 8.4)
≥ 30 kg/m^2 | 5264 | 8.6 (5.8 - 11.5)

Figure 7 shows a model of the rate of pregnancy as BMI increases based on data from Study 1. There is an increase in pregnancy rate (i.e., the number of pregnancies per 100 woman-years), as BMI increased based on the primary analysis population (N = 1,735). TWIRLA is contraindicated in women with a BMI ≥ 30 kg/m^2 [see Indications and Usage (1) and Contraindications (4)].

Figure 7. Pregnancy Rates (Estimated*) in TWIRLA-Treated Patients as BMI Increases for Women ≤ 35 Years of Age in Study 1

*Plot is based on Poisson Model with continuous BMI as the predictor (N=1,735); one woman in the primary analysis population had no BMI information. The solid line displays the estimated pregnancy rate, and the shaded area displays the 95% confidence interval for the estimated pregnancy rate.

Adhesion
Based on a Phase 1 study in 78 subjects wearing one TWIRLA on the lower abdomen for 7 days, 77 systems applied (98.7%) exhibited 75% or greater surface area adhesion at all timepoints evaluated (every 24 hours) throughout the wear period. In the Phase 3 trial, 5.0% of all transdermal systems worn during the year-long trial (55,900 transdermal systems) fully detached. Subject-reported adhesion was generally better for the abdomen as compared to the upper torso and buttock. Full detachment rates were higher for transdermal systems exposed to water as compared to transdermal systems with no water exposure.

16 HOW SUPPLIED/STORAGE AND HANDLING

16.1 How Supplied

TWIRLA (levonorgestrel and ethinyl estradiol) transdermal system is a beige 28 cm^2 round product etched with “TWIRLA Levonorgestrel 120 mcg/day Ethinyl Estradiol 30 mcg/day” and supplied as:

- a carton of 3 identical TDS, each TDS is packaged in an individual pouch. NDC 71671-100-03
- as a single TDS provided for replacement as needed. NDC 71671-100-01

16.2 Storage Conditions and Disposal

Store at room temperature 20°C to 25°C (68°F to 77°F) with excursions permitted 15°C to 30°C (59°F to 86°F) [see USP Controlled Room Temperature].

Store in original unopened pouch.

Used TDS still contain some active hormones. To discard, fold the sticky sides of the TDS together, place in a sturdy container, preferably with a child-resistant cap, and place this container in the trash. Used TDS should not be flushed down the toilet. See www.fda.gov/drugdisposal for more information about disposal of medicines.

17 PATIENT COUNSELING INFORMATION

Advise the woman to read the FDA-approved patient labeling (Patient Information and Instructions for Use).

Cigarette Smoking
Advise the woman that cigarette smoking increases the risk of serious cardiovascular events from CHC use. Women who are over 35 years old and smoke should not use TWIRLA [see Boxed Warning and Warnings and Precautions (5.1)].

Venous Thromboembolism
Advise the woman that there is an increased risk of VTE compared to non-users of CHCs is greatest after initially starting a CHC or restarting (following a 4-week or greater interruption in intake) the same or a different CHC.

Use during Pregnancy
TWIRLA is not to be used during pregnancy. Instruct the woman to stop TWIRLA if pregnancy is confirmed during treatment [see Contraindications (4)].

Sexually Transmitted Infections
Advise the woman that TWIRLA does not protect against HIV infection and other sexually transmitted infections.

Missed Dosing Instructions
Apply one TDS weekly for 3 weeks followed by one TDS free week. Instruct women what to do in the event TDS change is missed. See “What if you forget to change your patch (left your patch on more than 7 days)?” and “What if you forget to remove your patch for the patch free week?” in the FDA-approved patient labeling (Instructions for Use) [see Dosage and Administration (2.3)].

Need for Additional Contraception
Postpartum women who have not yet had a period when they start TWIRLA need to use an additional method of contraception until they have used the TDS for one week [see Dosage and Administration (2.1)].

A back-up or alternative method of contraception is needed when enzyme inducers are used with TWIRLA [see Drug Interactions (7.1)].

Lactation
TWIRLA may reduce breast milk production. This is less likely to occur if breast-feeding is well established. When possible, nursing women should use other methods of contraception until they have discontinued breast-feeding [see Use in Specific Populations (8.2)].

Amenorrhea and Possible Symptoms of Pregnancy
Amenorrhea may occur. Advise the woman to contact a health care provider in the event of amenorrhea in two or more consecutive cycles or in case of symptoms of pregnancy such as morning sickness or unusual breast tenderness [see Warnings and Precautions (5.9)].

Fertility following Discontinuation of TWIRLA
Resumption of fertility after discontinuing TWIRLA is expected.

Avoidance of TDS Detachment
Advise women to avoid frequent or prolonged water exposure (e.g., swimming) and also to avoid use of large amounts of body lotions or oils. Advise women to check the TDS for partial or complete TDS detachment not only daily but also after frequent or prolonged water exposure.

Manufactured by:
Corium International, Inc.
4558 50th Street, SE
Grand Rapids, MI 49512

Manufactured for:
Agile Therapeutics, Inc.
500 College Rd. E, Suite 310
Princeton, NJ 08540

PATIENT INFORMATION
TWIRLA® (TWER-la)
(levonorgestrel and ethinyl estradiol) transdermal system

What is the most important information I should know about TWIRLA?

- Do not use TWIRLA if you smoke cigarettes and are over 35 years old. Smoking increases your risk of serious cardiovascular side effects from combination hormonal contraceptives (CHCs), including death from heart attack, blood clots or stroke. This risk increases with age and the number of cigarettes you smoke.
- Do not use TWIRLA if your Body Mass Index (BMI) is 30 kg/m^2 or more. If you do not know what your BMI is, please talk to your health care provider. Women with a BMI of 30 kg/m^2 or more who use CHCs may have a higher risk for developing side effects like blood clots compared to women with a BMI lower than 30 kg/m^2.

Hormonal birth control methods help to lower the chances of becoming pregnant when taken as directed. TWIRLA does not protect against HIV infection (AIDS) and other sexually transmitted infections (STIs).

What is TWIRLA?

TWIRLA is:

- a birth control patch for women with a BMI less than 30 kg/m^2 who can become pregnant. It contains two female hormones, a progestin called levonorgestrel, and an estrogen called ethinyl estradiol. Birth control methods that have both an estrogen and a progestin are called combination hormonal contraceptives (CHCs).

TWIRLA is less effective in women with a BMI of 25 kg/m^2 or more.

How well does TWIRLA work?

Your chance of getting pregnant depends on how well you follow the directions for using TWIRLA. The better you follow the directions, the less chance you have of getting pregnant.

For TWIRLA to be most effective, you must use TWIRLA exactly as your healthcare provider tells you to. Each patch must be fully attached to the skin during the 7 days in order for it to work the best.

TWIRLA is less effective in women who have a BMI of 25 kg/m2 or more. If you have a BMI of 30 kg/m2 or more, talk to your healthcare provider about other methods of birth control which may be right for you.

Do not use TWIRLA if you:

- smoke and are over 35 years old.
- have or have had blood clots in your arms, legs, eyes or lungs.
- have had a stroke.
- have had a heart attack.
- have certain heart valve problems or heart rhythm problems that can cause blood clots to form in the heart.
- have a problem that makes your blood clot more than normal that you were born with (inherited) or that has happened for other reasons such as medicines, surgery or injuries (acquired).
- have high blood pressure that is not controlled.
- have diabetes and you are over the age of 35, have high blood pressure or have kidney, eye, nerve, or blood vessel damage, or have had diabetes for more than 20 years.
- have had certain kinds of severe migraine headaches with aura, numbness, weakness or changes in vision, or have any migraine headaches if you are over age 35.
- have a BMI of 30 kg/m^2 or more.
- have liver problems including liver tumors, hepatitis, cirrhosis, or liver disease.
- have unexplained vaginal bleeding.
- are pregnant or think you may be pregnant. However, TWIRLA is not known to cause birth defects when used by accident during pregnancy.
- have had breast cancer or any cancer that is sensitive to female hormones.
- are allergic to any of the ingredients in TWIRLA. See a complete list of ingredients at the end of this Patient Information leaflet. Symptoms of an allergic reaction you may include itching and irritation at the patch site.
- take any Hepatitis C drug combination containing ombitasvir, paritaprevir, ritonavir, with or without dasabuvir. This may increase levels of a liver enzyme called alanine aminotransferase (ALT) in the blood.

TWIRLA may not be a good choice for you if you have ever had jaundice (yellowing of the skin or eyes) caused by pregnancy (also called cholestasis of pregnancy) or related to previous use of hormonal birth control.

Tell your healthcare provider if you have ever had any of the above conditions. Your healthcare provider may recommend another method of birth control.

Before using TWIRLA, tell your healthcare provider about all of your medical conditions, including if you:

- are pregnant or think you are pregnant. TWIRLA is not for pregnant women. If you think you are pregnant, you should have a pregnancy test and know the results. Do not use TWIRLA if the test is positive and talk to your healthcare provider.
- are scheduled for surgery. TWIRLA may increase your risk of blood clots after surgery. You should stop using your TWIRLA patch at least 4 weeks before you have surgery and not restart it until at least 2 weeks after your surgery.
- have or have had gallbladder problems including yellowing of the skin or eyes during pregnancy.
- have high cholesterol that is not controlled.
- have or have had depression.
- have a history of hereditary angioedema.
- have had dark patches of skin on your forehead, cheeks, upper lip, and chin (chloasma).
- are breastfeeding or plan to breastfeed. CHC medicines that contain estrogen, like TWIRLA, may decrease the amount of milk you make. A small amount of hormones from the TWIRLA patch may pass into your breast milk. You may want to use another method of birth control until you are ready to stop breastfeeding.

Tell your healthcare provider about all the medicines you take, including prescription and over-the-counter medicines, vitamins, and herbal supplements. Some medicines and herbal products may make TWIRLA less effective or cause breakthrough bleeding, including, but not limited to:

- certain anti-seizure medicines (such as barbiturates, carbamazepine, felbamate, oxcarbazepine, phenytoin, rufinamide, or topiramate).
- medicine to treat chemotherapy-induced nausea and vomiting (aprepitant).
- medicine to treat high blood pressure in the vessels of the lung (bosentan).
- a certain medicine used to treat fungal infections (griseofulvin).
- certain combinations of HIV medicines (nelfinavir, ritonavir, darunavir/ritonavir, (fos)amprenavir/ritonavir, lopinavir/rotinavir, and tipranavir/ritonavir).
- certain non-nucleoside reverse transcriptase inhibitors (such as nevirapine and efavirenz).
- rifampin and rifabutin.
- certain hepatitis C (HCV) medicines (such as boceprevir, telaprevir).
- St. John’s wort.
- Use another birth control method (such as condoms and spermicide, or diaphragm and spermicide) when you take medicines that may make TWIRLA less effective and for 28 days after stopping the medicine.
- Some medicines and grapefruit juice may increase your level of the hormone ethinyl estradiol if used together, including:
  - the pain reliever acetaminophen.
  - ascorbic acid (vitamin C).
  - certain medicines used to treat fungal infections (itraconazole, ketoconazole, voriconazole, and fluconazole).
  - certain HIV medicines (atazanavir/ritonavir, indinavir).
  - non-nucleoside reverse transcriptase inhibitors (such as etravirine).
  - medicines to lower cholesterol (such as atorvastatin and rosuvastatin).
- TWIRLA may affect the way that lamotrigine, a medicine used to treat seizures, works and may increase the risk of seizures. Your healthcare provider may need to adjust the dose of lamotrigine while you are on TWIRLA.
- If you are scheduled for any laboratory tests, tell your healthcare provider that you are using TWIRLA. Certain blood tests may be affected by CHC methods.
- Women on thyroid replacement therapy may need increased doses of thyroid replacement medicine or corticosteroid replacement medicine may need increased doses of their thyroid hormone or cortisol medicines.

Ask your healthcare provider if you are not sure if you take any of the medicines listed above.

Know the medicines you take. Keep a list of them to show your healthcare provider and pharmacist when you get a new medicine. Talk to your healthcare provider before you start taking a new medicine.

How should I use TWIRLA?

- For detailed instructions, see the step-by-step instructions for using TWIRLA at the end of this Patient Information leaflet.
- Use TWIRLA exactly as your healthcare provider tells you to use it.
- Wear 1 TWIRLA patch at a time.
- Do not skip using any TWIRLA patches, even if you do not have sex often.
- TWIRLA is applied in a 4 week patch cycle. Each patch cycle includes 4 weeks (28 days). You will put on 1 patch every week for 3 weeks. You will not wear a patch during week 4. Each patch is worn for 7 days (1 week).
- Apply a new TWIRLA patch on the same day each week (this is called your Patch Change Day). For example, if you apply your first patch on a Monday, all of your TWIRLA patches should be applied on Monday.
- You will not wear a TWIRLA patch during week 4 (this is called your Patch Free Week). Make sure you remove the old patch from your body. Your period should begin during your Patch Free Week. After you have finished week 4, apply a new TWIRLA patch on the day after Week 4 ends. Repeat the patch cycle of 1 patch a week for 3 weeks followed by your Patch Free Week.
- Do not cut, damage or change the TWIRLA patch in any way. If the patch is cut, damaged or changed in any way, it may be less effective.
- Your TWIRLA patch should never be off more than 7 days in a row. If you ever go more than 7 days without a patch, you should use another non-hormonal back up birth control method.
- If you miss your Patch Change Day, put the patch on late or if it comes off of your skin before your Patch Change Day, you may or may not need to use another non-hormonal back up birth control method. See the detailed table in the Instructions for Use for more information.
- If you miss a period you might be pregnant. Some women miss their periods or have light periods on hormonal birth control methods even when they are not pregnant. Call your healthcare provider if you miss 1 period and have not used your TWIRLA patch every day or you miss 2 periods in row.

What should I avoid while using TWIRLA?

- Smoking
- The following can cause the patch to not stick the right way making TWIRLA less effective:
- Avoid using makeup, creams, lotions, oils, powders or any other products on the skin area where you put or plan to put the patch.
- Swimming or contact with water often or for long periods of time (30 minutes or more). Talk with your healthcare provider about the best method of birth control if you are a swimmer or you often come in contact with water for 30 minutes or more.
- Women who tend to get chloasma should avoid spending a long time in sunlight, tanning booths, and under sun lamps while using TWIRLA. Use sunscreen if you have to be in the sunlight.

What are the possible side effects of TWIRLA?

TWIRLA may cause serious side effects, including:

- See “What is the most important information I should know about TWIRLA?”
- blood clots. Like pregnancy, hormonal birth control may increase the risk of serious blood clots (see following graph), especially in women who have other risk factors, such as smoking, high blood pressure, high levels of fat in the blood, diabetes, obesity, a family history of blood clots or are older than 35 years old. This increased risk is highest when you first start using hormonal birth control and when you restart the same or different hormonal birth control after not using it for a month or more. Some studies have reported that women who use levonorgestrel and ethinyl estradiol transdermal system have a higher risk of getting a blood clot. Talk to your healthcare provider about your risk of getting a blood clot before using TWIRLA or deciding which type of birth control is right for you.

It is possible to die or be permanently disabled from a problem caused by a blood clot, such as a heart attack or a stroke. Some examples of serious blood clots are blood clots in the:

- legs (deep vein thrombosis)

- lungs (pulmonary embolus)

- eyes (loss of eyesight)

- heart (heart attack)

- brain (stroke)

- To put the risk of developing a blood clot into perspective: If 10,000 women who are not pregnant and do not use hormonal birth control are followed for one year, between 1 and 5 of these women will develop a blood clot. The figure below shows the likelihood of developing a serious blood clot for women who are not pregnant and do not use hormonal birth control, for women who use hormonal birth control, for pregnant women, and for women in the first 12 weeks after delivering a baby.

Likelihood of Developing a Serious Blood Clot (Venous Thromboembolism [VTE])

*CHC = combination hormonal contraception

**Pregnancy data based on actual duration of pregnancy in the reference studies. Based on a model assumption that pregnancy duration is nine months, the rate is 7 to 27 per 10,000 Woman Years (WY).

Call your healthcare provider right away if you have:

ο leg pain that does not go away

ο sudden shortness of breath
ο sudden changes to your vision or blindness
ο severe pain or pressure in your chest
ο sudden, severe headache unlike your usual headaches
ο weakness or numbness in an arm or leg
ο trouble speaking

- liver problems, including liver tumors. Stop using TWIRLA and tell your healthcare provider right away if you have yellowing of your skin or eyes (jaundice).
- high blood pressure. Your healthcare provider will check your blood pressure and may stop you from using TWIRLA if your blood pressure rises.
- gallbladder problems or worsening of a gallbladder problem you already have. You may have an increased risk of gallbladder problems with the use of TWIRLA especially if you have had gallbladder problems before or gallbladder problems when you were pregnant.
- headaches. Headaches can be a common but serious side effect. Tell your healthcare provider if you have new headaches that keep coming back, that do not go away, or are severe. Also tell your healthcare provider if your migraine headaches happen more often or are more severe than normal. Your healthcare provider may stop you from using TWIRLA.
- irregular or unusual vaginal bleeding and spotting between your menstrual periods or absence of menstrual periods (amenorrhea). This can happen especially during the first 3 months of using TWIRLA. You also may have no bleeding at all. Tell your healthcare provider if you miss 2 or more menstrual cycles. After you stop using TWIRLA, your periods may not happen as often or you may have no bleeding at all, especially if you had these types of menstrual cycles before taking TWIRLA.
- depression.
- swelling of your skin especially around your mouth, eyes, and in your throat (angioedema). Call your healthcare provider or get emergency medical care right away if you have a swollen face, lips, mouth, tongue or throat as this may lead to difficulty swallowing or breathing. Your risk of having angioedema is higher if you have a history of angioedema.
- dark patches of skin on your forehead, cheeks, upper lip, and chin (chloasma). Your risk of getting chloasma with the use of TWIRLA is higher if you had chloasma during pregnancy.

The most common side effects of TWIRLA include:

- skin reactions at the patch site such as bumps, redness or changes in color of your skin, bleeding itching, rash, dryness, pain and swelling.

- headache

- weight gain

- nausea

- menstrual cramps

These are not all the possible side effects of TWIRLA.

Call your doctor for medical advice about side effects. You may report side effects to FDA at 1-800-FDA-1088.

How should I store TWIRLA?

- Store at room temperature between 68°F to 77°F (20°C to 25°C).
- Store TWIRLA in the original unopened pouch it comes in. Apply TWIRLA immediately after taking it out from the pouch.
- Do not store TWIRLA in the refrigerator or freezer.
- Used TWIRLA patches may still have some active hormones. To throw away the TWIRLA patch, fold the sticky side of the patch together, and place this container in the trash. Do not flush used TWIRLA patches down the toilet.

Keep TWIRLA and all medicines out of the reach of children.

General information about the safe and effective use of TWIRLA.

Medicines are sometimes prescribed for purposes other than those listed in a Patient Information leaflet. Do not use TWIRLA for a condition for which it was not prescribed. Do not give TWIRLA to other people. It may harm them. You can ask your pharmacist or healthcare provider for information about TWIRLA that is written for health professionals.

Does hormonal birth control cause cancer?

It is not known if hormonal birth control causes breast cancer. Some studies, but not all, suggest that there could be a slight increase in the risk of breast cancer among current users with longer duration of use.

If you have breast cancer now, or have had it in the past, do not use hormonal birth control because some breast cancers are sensitive to hormones.

Women who use hormonal birth control may have a slightly higher chance of getting cervical cancer. However, this may be due to other reasons such as an increased number of sexual partners.

What should I know about my period when using TWIRLA?

When you use TWIRLA you may have bleeding and spotting between periods, called unplanned bleeding. Unplanned bleeding may vary from light slight staining between menstrual periods to breakthrough bleeding which is a flow much like a regular period. Unplanned bleeding occurs most often during the first few months of hormonal contraceptive use but may also occur after you have been using the patch for some time. Such bleeding may be temporary and usually does not indicate any serious problems. It is important to continue using the patch on schedule. If the unplanned bleeding or spotting occurs in more cycles, is unusually heavy, or lasts for more than a few days, talk to your healthcare provider.

What if I miss my scheduled period when using TWIRLA?

You should consider the possibility that you are pregnant if you miss your scheduled period. Because scheduled periods may not happen as often when you are using TWIRLA, tell your healthcare provider that you have missed your period and that you are using TWIRLA. Also, notify your healthcare provider if you have symptoms of pregnancy such as morning sickness or unusual breast tenderness. It is important that your healthcare provider checks to see if you are pregnant. Stop using TWIRLA if you are pregnant.

What if I want to become pregnant?

You may stop using TWIRLA whenever you wish. Consider a visit with your healthcare provider for a pre-pregnancy check-up before you stop using TWIRLA.

What are the ingredients in TWIRLA?

Active ingredients: levonorgestrel (a progestin) and ethinyl estradiol (an estrogen)

Inactive ingredients: polyester release liner, woven polyester backing membrane, acrylic adhesives, polyester internal membrane, polyisobutylene adhesives, copovidone, polybutene, crospovidone, lauryl lactate, dimethyl sulfoxide, capric acid, and ethyl lactate.

INSTRUCTIONS FOR USE

TWIRLA® (TWER-la)

(levonorgestrel and ethinyl estradiol) transdermal system

TWIRLA is for skin use only.

Read this Instructions for Use before you start using the TWIRLA transdermal system (TDS) (also called a patch) and each time you get a refill. There may be new information. This information does not take the place of talking to your healthcare provider about your contraceptive treatment.

Do not cut, damage or change the TWIRLA patch in any way. If the patch is cut, damaged or changed in any way, it may be less effective.

Starting TWIRLA for the first time: If you are starting TWIRLA for the first time, you should wait until you begin your menstrual period.

- Day 1 Start. You should apply your first patch during the first 24 hours of your menstrual period. Your Patch Change Day will be on this day every week. If you start after Day 1 of your menstrual period, non-hormonal back up birth control (such as condoms and spermicide, or diaphragm and spermicide) should be used in addition to the patch for the first 7 days of your first patch cycle.

If you are changing from the oral hormone birth control pills, vaginal contraceptive ring or another transdermal patch to TWIRLA:

- Day 1 Start: You should apply your first patch during the first 24 hours of your menstrual period. Your Patch Change Day will be on this day every week. If you start after Day 1 of your menstrual period, non-hormonal back up birth control (such as condoms and spermicide, or diaphragm and spermicide) should be used in addition to the patch for the first 7 days of your first patch cycle.

- Finish your current oral hormone birth control pill cycle, vaginal ring cycle or other transdermal patch cycle. Apply your first TWIRLA patch on the day you would normally start your next oral birth control pill, patch or insert your next vaginal ring.

- If you do not get your period within 1 week after taking your last active oral hormone birth control pill, removing your last vaginal ring or other transdermal patch cycle, check with your healthcare provider to make sure you are not pregnant. You may still go ahead and start TWIRLA for contraception.

- If you apply your TWIRLA patch more than 1 week after taking your last active oral hormone birth control pill, removing your last vaginal ring or other transdermal patch cycle use a non-hormonal contraceptive method with the TWIRLA patch for the first 7 days of using the patch.

If you are starting TWIRLA after a miscarriage or abortion:

- You may start TWIRLA right away after a miscarriage or abortion that occurs in the first 12 weeks (first trimester) of pregnancy. If you start TWIRLA within 5 days of your first trimester abortion or miscarriage, you do not need to use another back up contraceptive method.

- If you do not start TWIRLA within 5 days after a first trimester miscarriage or abortion, use a non-hormonal contraceptive method of birth control, such as a condom and spermicide or diaphragm and spermicide, while you wait for your period to start.

- If you are starting TWIRLA after a miscarriage or abortion that occurs after the first 12 weeks of pregnancy (second trimester), wait 4 weeks before using TWIRLA and use a non-hormonal contraceptive method of birth control, such as a condom and spermicide or diaphragm and spermicide, for the first 7 days of your first patch cycle only.

If you are starting TWIRLA after childbirth:

- If you are not breastfeeding, wait 4 weeks before using TWIRLA and use a non-hormonal contraceptive method of birth control, such as a condom and spermicide or diaphragm and spermicide, for the first 7 days of your first patch cycle only. If you start using TWIRLA after childbirth and have not had your menstrual period, tell your healthcare provider. They will need to make sure you are not ovulating or pregnant before starting TWIRLA. If your healthcare provider tells you are not pregnant, use a non-hormonal contraceptive method for the first 7 days of patch of your first patch cycle.

How to Apply TWIRLA:

Where should the patch be applied?

- Wear only 1 patch at a time.
- Before applying the patch, make sure your skin is clean and dry.
- Avoid using make up, creams, lotions, oils, powders or any other products on the skin area where you put or plan to put the patch.
- Application sites to apply the patch include the lower stomach area (abdomen), buttock, or the upper torso. See diagrams above.
- When you put the patch on, it should lay flat and smooth with no wrinkles or folds.
- On Patch Change Day, remove the current patch and immediately put on a new patch. Do not apply the new patch directly over skin where the old patch site was. You should use a new application site.

Where not to place the patch.

- Do not put the patch on your waistline or near clothing or undergarment seams.
- Do not put the patch on the breasts, on cut or irritated skin (rashes or other skin problems), or on the same location as the old patch.

Patch Application Instructions

- Before the patch is applied, make sure your skin is clean and dry. Also make sure you have not used any make up, creams, lotions, oils, powders or any other products on the skin area where you put or plan to put the patch
- Each patch is individually sealed in a pouch.
- It is important that you immediately apply the patch after being removed from the pouch.

Step 1. Tear the pouch open at the notch on the pouch.

Step 2. Open the pouch and carefully remove the patch. The patch is attached to a clear protective liner.

Avoid touching the sticky side of the patch

Step 3a. Hold the patch with the clear protective liner facing you. You will see two sections: a large section and a small section.

Avoid touching the sticky side of the patch with your fingers.

Step 3b. Hold the small section of the liner. Remove and throw away (discard) the large section of the liner while still holding the small section of the liner.

Step 4. Hold the small section of the liner and apply the sticky side of the patch to the chosen patch site.

Step 5. Press the sticky side of the patch firmly onto your skin and smooth it down.

Avoid wrinkles or folds

Step 6. If the patch is not flat on the skin or there are large wrinkles, gently pull the patch off the skin while holding only the remaining protective liner and then put it on again.

Step 7. After the patch is flat with no wrinkles, pull an edge of the remaining protective liner and gently pull it off.

Step 8a. After the patch is on your body, press the entire patch firmly into place with your hand for 10 seconds, making sure the edges stick well.

Step 8b. Make sure the patch is on your skin all the way.

Step 9. The edges of the patch should be smoothed over with your finger and make sure there is good contact around the patch with your skin and make sure there are no wrinkles.

Step 10. It is important that you check the patch every day to make sure it is in the right place. The patch should be checked after any water exposure (such as bathing, showering, or swimming) to make sure it is in the right place because water may affect how well the patch sticks to your skin.

How do I throw away TWIRLA patches?

- To throw away your TWIRLA patch, fold the sticky side of the patch together and place in the trash right away so that children and pets cannot reach it. Do not flush used TWIRLA patches down the toilet.

- For more information on how to safely throw away medicines, see www.fda.gov/drugdisposal.

When should I change the TWIRLA patch?

- TWIRLA is applied in a 4 week patch cycle. Each patch cycle includes 4 weeks (28 days). You will put on 1 patch every week for 3 weeks. You will not wear a patch during week 4. Each patch is worn for 7 days (1 week).

- Apply a new TWIRLA patch on the same day each week (this is called your Patch Change Day). For example, if you apply your first patch on a Monday, all of your TWIRLA patches should be applied on Monday.

- You will not wear a TWIRLA patch during week 4 (this is called your Patch Free Week). Make sure you remove the old patch from your body. Your period should begin during your Patch Free Week.

- After you have finished week 4, apply a new TWIRLA patch on the day after Week 4 ends. Repeat the patch cycle of 1 patch a week for 3 weeks followed by your Patch Free Week.

What if a patch starts to lift off your skin or completely comes off?

- If your patch starts to lift off your skin or completely comes off and you do not replace it, you may not get enough hormones to keep you from getting pregnant.

- If a patch starts to lift off your skin or is completely off for less than one day (up to 24 hours), you should try and put it on again to the same place or replace it with a new patch immediately. No back up birth control is needed and your Patch Change Day will remain the same.

- If a patch starts to lift off your skin or is completely off for more than 1 day (24 hours or more) or if you are not sure how long the patch has been not attached to your skin, you may not be protected from pregnancy. You should stop your current patch cycle and start over on a new patch cycle right away by putting on a new patch. The day you apply your new patch is now your new Day 1 and your new Patch Change Day. Non-hormonal back up birth control, (such as condoms and spermicide, or diaphragm and spermicide) must be used for the first week of the new patch cycle.

- Do not put a patch on again if it is no longer sticky, if it has become stuck to itself or another surface or if it has other material stuck to it. If your patch cannot be put on again, a new patch should be put on right away. If you need help applying a patch, contact Agile Medical Information at 1-855-389-4752 or email: medicalaffairs@agiletherapeutics.com.

Can I wear the patch when I am exercising, or using a sauna, swimming pool, or whirlpool?

- Yes, women can maintain all their normal daily activities while using the patch.

- It is important to check your patch after any water that touches your patch during bathing, showering, or swimming, as prolonged water exposure may affect how well the patch sticks to your skin.

- If the patch starts to come off or completely lifts off the skin, try to put it on again.

- A patch should not be put on again if it is no longer sticky, if it has become stuck to itself or another surface or if it has other material stuck to it.

- If your current patch cannot be put on again, a new patch should be put on right away. Before applying the patch, make sure your skin is clean and dry.

- Make sure you have not used any make up, creams, lotions, oils, powders or any other products on the skin area where you put or plan to put the patch. If you find yourself in need of an additional patch because you needed to replace a patch, contact Agile Medical Information at 1-855-389-4752 or email: medicalaffairs@agiletherapeutics.com.

What if you forget to change your patch (left your patch on more than 7 days)?

- If you forget to change your patch at the start of any patch cycle (Day 1): You may not be protected from pregnancy. You should apply the first patch of your new patch cycle as soon as you remember. This is now your new Patch Change Day and your new Day 1. You must use non-hormonal back up birth control (such as condoms and spermicide, or diaphragm and spermicide) for the first week of your new patch cycle.

- If you forget to change your patch in the middle of the patch cycle (Day 8 or Day 15): for 1 or 2 days (up to 48 hours): you should apply a new patch right away. The next patch should be applied on your usual Patch Change Day. No back up birth control is needed.

- If you forget to change your patch for more than 2 days (48 hours or more): You may not be protected from pregnancy. You should stop your current patch cycle and start a new 4 week patch cycle right away by putting on a new patch. This is now your new Patch Change Day and your new Day 1. You must use non-hormonal back up birth control for the first week of your new patch cycle.

What to do if the patch starts to lift or the patch completely comes off from the skin and Late or Missed Patch Applications
Frequent Patch Situations | Will I have a New Patch- Change Day | Will I need to start a New 4 week Patch Cycle | Will I need a backup Birth Control method
Did not apply patch on scheduled Day 1 of new patch cycle | Yes | Yes | Yes (for 7 days)
Patch not attached for less than 24 hours | No | No | No
Patch not attached for 24 hours or more, or unsure how long | Yes | Yes | Yes (for 7 days)
Less than 48 hours late for Patch Change Day (Day 8 or 15) | No | No | No
48 hours or more late for Patch Change Day (Day 8 or 15) | Yes | Yes | Yes (for 7 days)
Forgets to remove last patch on Day 22 | No | No | No

What if you forget to remove your patch for the patch free week?

- Past Day 22: You should take it off as soon as you remember. No other change is needed. You should still start the next patch cycle on the usual Patch Change Day, which is the day after Day 28. No back up birth control is needed.

- Your TWIRLA patch should never be off more than 7 days in a row. If you ever go more than 7 days without a patch, you should use another birth control method.

- As with all hormonal birth control, the risk of getting pregnant increases with each day you go past the recommended 7 day patch free period.

What if you wish to change your Patch Change Day?

- If you want to change your Patch Change Day you should complete your current patch cycle, removing the third patch on the correct day. During the Patch Free Week, you may select an earlier Patch Change Day by applying a new patch on the chosen day.

Your TWIRLA patch should never be off more than 7 days in a row.

Manufactured by:
Corium International, Inc.
4558 50th Street, SE
Grand Rapids, MI 49512

Manufactured for:
Agile Therapeutics, Inc.
500 College Rd. E, Suite 310
Princeton, NJ 08540

For more information call 1-855-389-4752 or email: medicalaffairs@agiletherapeutics.com.

This Instructions for Use has been approved by the U.S. Food and Drug Administration | Approved: 04/2022

Primary Panel - Pouch (Contains 1 transdermal system)

TwirlaTM
(levonorgestrel and ethinyl estradiol)
transdermal system
120 mcg/day levonogestrel and 30 mcg/day ethinyl estradiol

Contains 1
transdermal
system

NDC 71671-100-11

Each 28 cm^2 system contains 2.6 mg levonorgestrel (LNG) and 2.3 mg ethyinyl estradiol
(EE). The inactive components are acrylic adhesives, capric acid, copovidone,
crospovidone, dimethyl sulfoxide, ethyl lactate, lauryl lactate, polyester backing,
polyester release liner, polyisobutylene adhesive, and woven polyester fabric.

This product is intended to prevent pregnancy. It does not protect against HIV
(AIDS) and other sexually trasmitted diseases.

Rx only. For Transdermal Use Only.

Keep out of reach of children. Package not child resistant.
Store at room temperature 20°C to 25°C (68°F to 77°F) with excursions permitted
to 15°C to 30°C (59°F to 86°F).

Recommended Dosage: See prescribing information. Apply immediately upon removal
from pouch. Each transdermal system is intended to be worn for 7 days - Fold used
system and discard prior to applying new system.

Mfd. For: Agile Therapeutics, Inc.
Princeton, NJ 08540
Mfd. By: Corium, Inc.
Grand Rapids, MI 49512

CAW1011

Primary Panel - Carton (Contains 3 transdermal systems)

NDC 71671-100-03

TwirlaTM
(levonorgestrel and ethinyl estradiol)
transdermal system
120 mcg/day levonogestrel and 30 mcg/day ethinyl estradiol

Contents: 3 transdermal systems

Each 28 cm^2 system contains 2.6 mg levonorgestrel (LNG) and 2.3 mg
ethyinyl estradiol (EE). The inactive components are acrylic adhesives, capric
acid, copovidone, crospovidone, dimethyl sulfoxide, ethyl lactate, lauryl
lactate, polyester backing, polyester release liner, polyisobutylene adhesive,
and woven polyester fabric.

This product is intended to prevent pregnancy. It does not protect against
HIV (AIDS) and other sexually trasmitted diseases.

Rx only. For Transdermal Use Only.

Agile® THERAPEUTICS

Primary Panel - Carton (Contains 1 transdermal system)

REPLACEMENR
ONLY-
UP TO 1 WEEK
THERAPY

NDC 71671-100-01

TwirlaTM
(levonorgestrel and ethinyl estradiol)
transdermal system
120 mcg/day levonogestrel and 30 mcg/day ethinyl estradiol

Contents: 1 replacement transdermal system

Each 28 cm^2 system contains 2.6 mg levonorgestrel (LNG) and 2.3 mg
ethyinyl estradiol (EE). The inactive components are acrylic adhesives, capric
acid, copovidone, crospovidone, dimethyl sulfoxide, ethyl lactate, lauryl
lactate, polyester backing, polyester release liner, polyisobutylene adhesive,
and woven polyester fabric.

This product is intended to prevent pregnancy. It does not protect against
HIV (AIDS) and other sexually trasmitted diseases.

Rx only. For Transdermal Use Only.

Agile® THERAPEUTICS